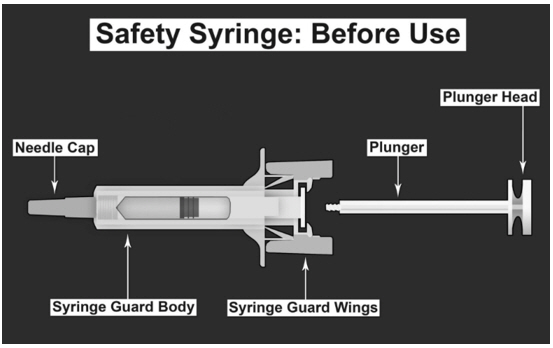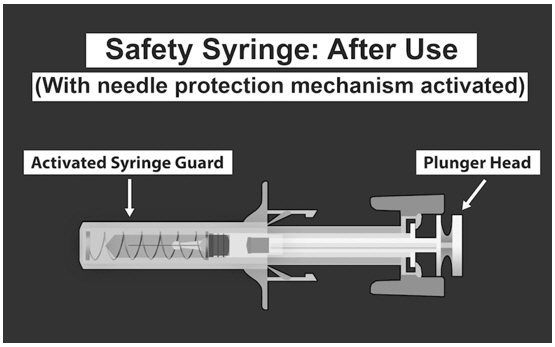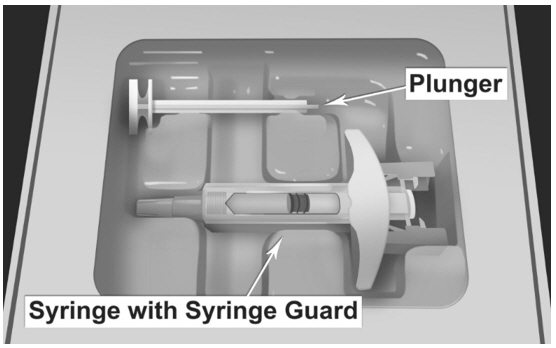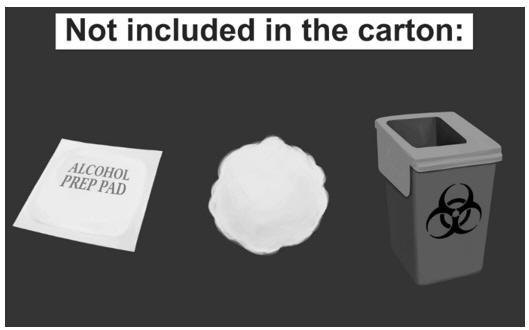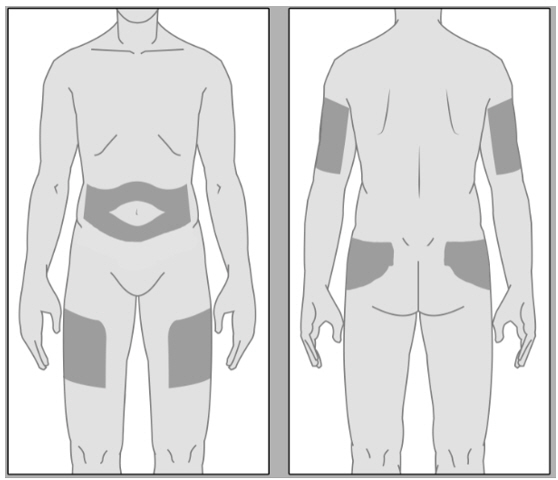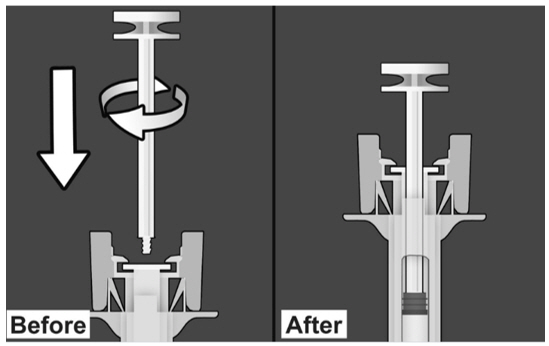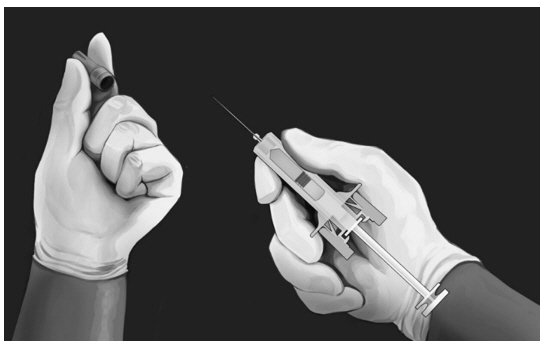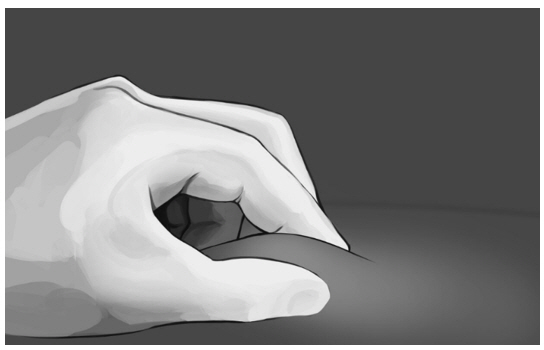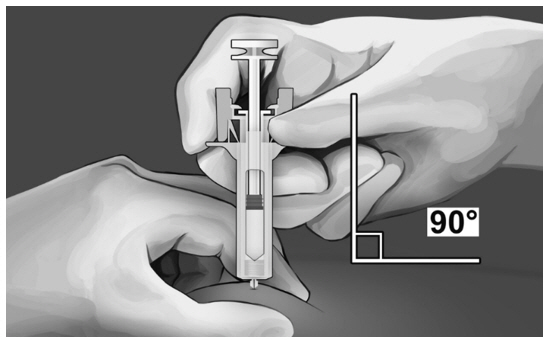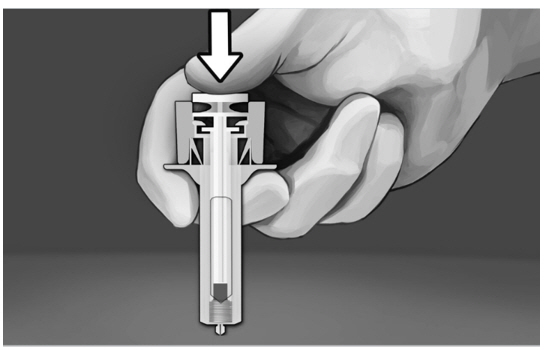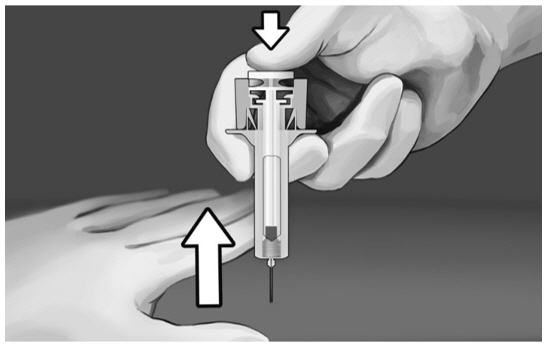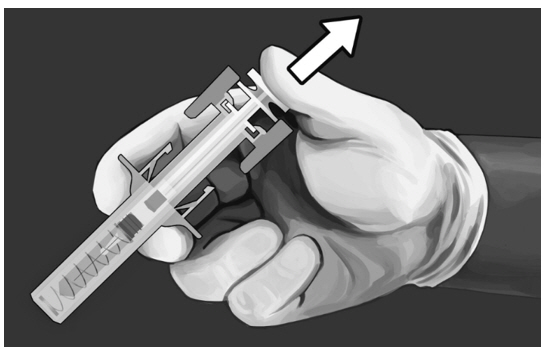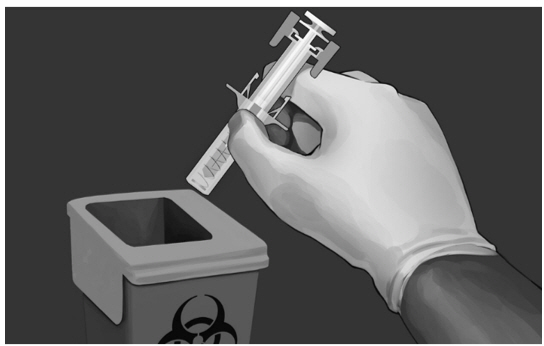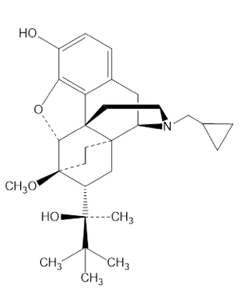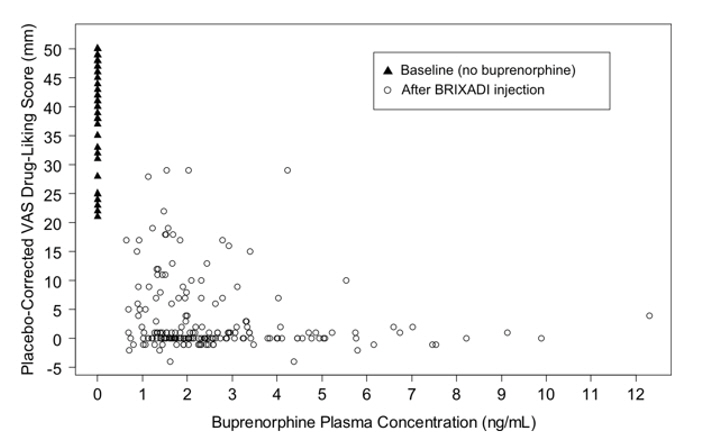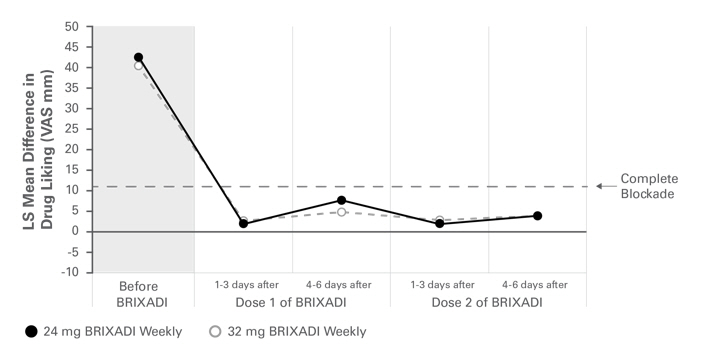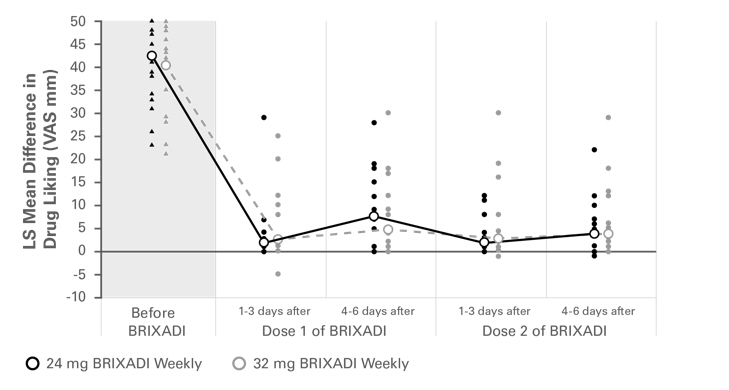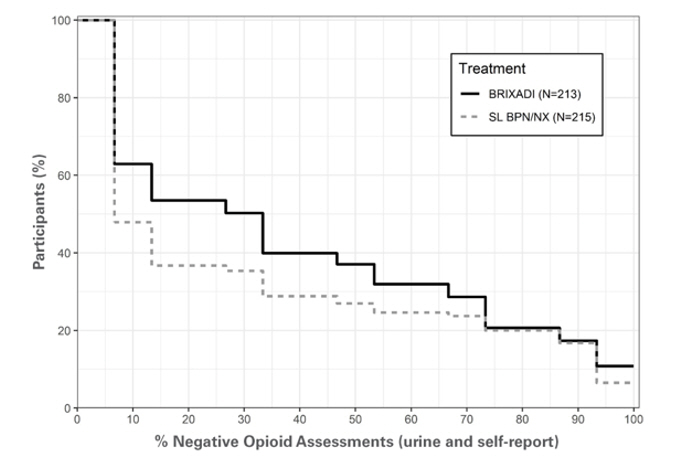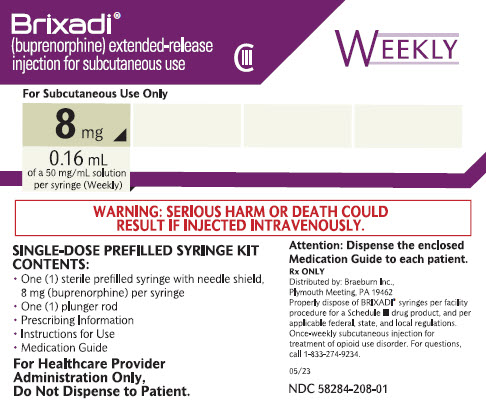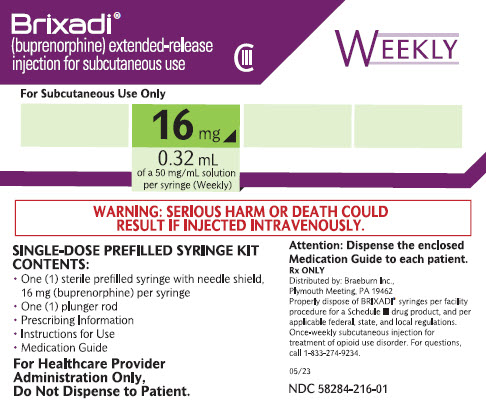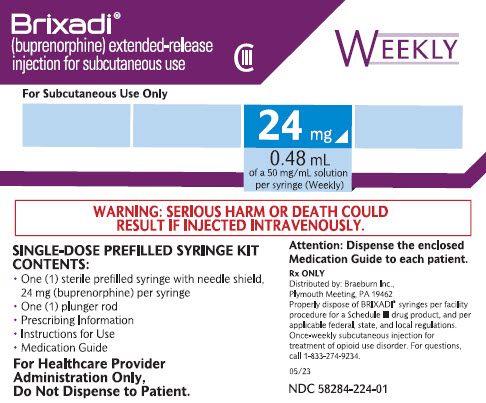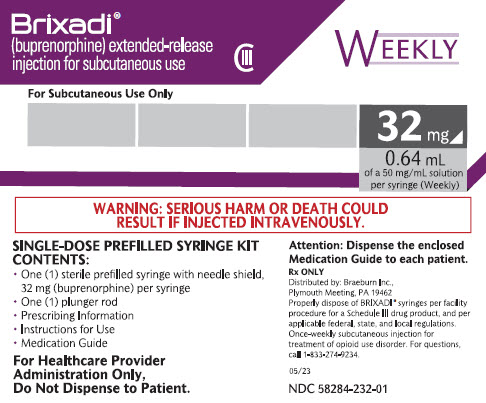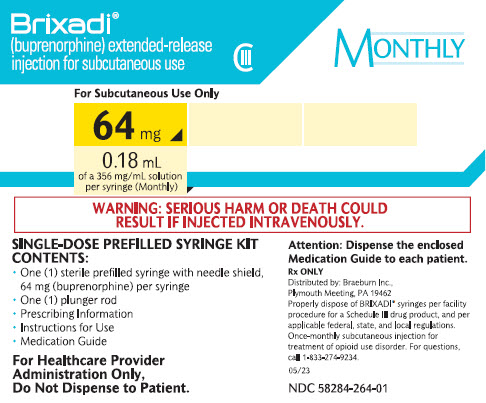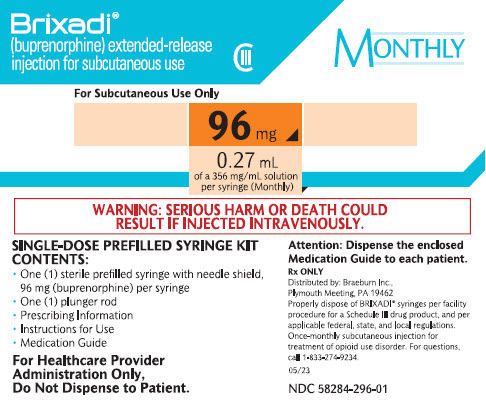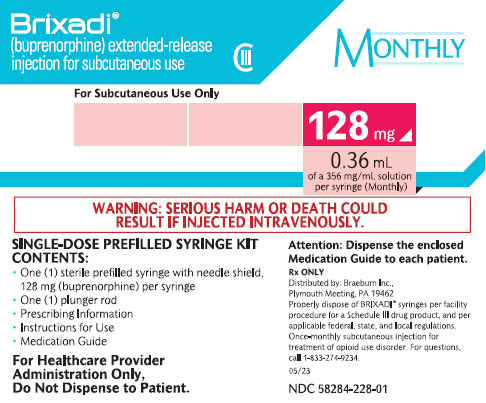 DRUG LABEL: BRIXADI
NDC: 58284-208 | Form: INJECTION
Manufacturer: Braeburn Inc.
Category: prescription | Type: HUMAN PRESCRIPTION DRUG LABEL
Date: 20251231
DEA Schedule: CIII

ACTIVE INGREDIENTS: BUPRENORPHINE 8 mg/0.16 mL
INACTIVE INGREDIENTS: ALCOHOL; LECITHIN, SOYBEAN; GLYCERYL DIOLEATE

HIGHLIGHTS OF PRESCRIBING INFORMATION

These highlights do not include all the information needed to use BRIXADI safely and effectively. See full prescribing information for BRIXADI.
BRIXADI® (buprenorphine) extended-release injection for subcutaneous use CIII
Initial U.S. Approval: 2002

WARNING: RISK OF SERIOUS HARM OR DEATH WITH INTRAVENOUS ADMINISTRATION; BRIXADI RISK EVALUATION AND MITIGATION STRATEGY

See full prescribing information for complete boxed warning.

- Serious harm or death could result if administered intravenously. (5.1)
- BRIXADI is only available through a restricted program called the BRIXADI REMS. Healthcare settings and pharmacies that order and dispense BRIXADI must be certified in this program and comply with the REMS requirements. (5.2)

RECENT MAJOR CHANGES

Dosage and Administration (2.2) 12/2025
Warnings and Precautions (5.4, 5.5) 12/2025

1 INDICATIONS AND USAGE

BRIXADI contains buprenorphine, a partial opioid agonist.

BRIXADI is indicated for the treatment of moderate to severe opioid use disorder in patients who have initiated treatment with a single dose of a transmucosal buprenorphine product or who are already being treated with buprenorphine. (1)

BRIXADI should be used as part of a complete treatment plan that includes counseling and psychosocial support. (1)

2 DOSAGE AND ADMINISTRATION

- Only healthcare providers should prepare and administer BRIXADI. (2.1)
- BRIXADI (weekly) and BRIXADI (monthly) are different formulations. Doses of BRIXADI (weekly) cannot be combined to yield an equivalent BRIXADI (monthly) dose. (2.1)
- BRIXADI should be injected slowly, into the subcutaneous tissue of the buttock, thigh, abdomen, or upper arm (2.1)
- Strongly consider recommending or prescribing an opioid overdose reversal agent (e.g., naloxone, nalmefene) at the time BRIXADI is initiated or renewed because patients being treated for opioid use disorder have the potential for relapse, putting them at risk for opioid overdose. (2.2)
- Injection sites for BRIXADI (weekly) should be alternated/rotated for each injection. (2.7)

See Full Prescribing Information for administration instructions. (2.7)

3 DOSAGE FORMS AND STRENGTHS

BRIXADI is a weekly and monthly injection provided in a pre-filled single-dose syringe with a 23 gauge ½ inch needle. (3)

- BRIXADI (weekly) is available in 8 mg/0.16 mL, 16 mg/0.32 mL, 24 mg/0.48 mL, and 32 mg/0.64 mL;
- BRIXADI (monthly) is available in 64 mg/0.18 mL, 96 mg/0.27 mL, and 128 mg/0.36 mL.

4 CONTRAINDICATIONS

Hypersensitivity to buprenorphine or any other ingredients in BRIXADI. (4)

5 WARNINGS AND PRECAUTIONS

- Addiction, Abuse, and Misuse: Buprenorphine can be abused in a manner similar to other opioids. Monitor patients for conditions indicative of diversion or progression of opioid dependence and addictive behaviors. (5.3)
- Respiratory Depression: Life-threatening respiratory depression and death have occurred in association with buprenorphine. Warn patients of the potential danger of self-administration of benzodiazepines or other CNS depressants while under treatment with BRIXADI. (5.4, 5.5)
- Neonatal Opioid Withdrawal Syndrome: Neonatal opioid withdrawal syndrome (NOWS) is an expected and treatable outcome of prolonged use of opioids during pregnancy. (5.6)
- Adrenal Insufficiency: If diagnosed, treat with physiologic replacement of corticosteroids, and wean patient off of the opioid. (5.7)
- Risk of Opioid Withdrawal with Abrupt Discontinuation: If treatment with BRIXADI is discontinued, monitor patients for withdrawal and treat appropriately. (5.8)
- Risk of Hepatitis, Hepatic Events: Monitor liver function tests prior to and during treatment. (5.9)
- Latex Allergy: The packaging of this product contains natural rubber latex which may cause allergic reactions. (5.10)
- Risk of Withdrawal in Patients Dependent on Full Agonist Opioids: Administer a test dose of transmucosal buprenorphine and monitor for precipitated withdrawal before injecting BRIXADI. (5.11)
- Treatment of Emergent Acute Pain: Treat pain with a non-opioid analgesic whenever possible. If opioid therapy is required, monitor patients closely because higher doses may be required for analgesic effect. (5.12)

6 ADVERSE REACTIONS

Adverse reactions commonly associated with BRIXADI administration (in ≥5% of patients) were injection site pain, headache, constipation, nausea, injection site erythema, injection site pruritus, insomnia, and urinary tract infection. (6.1)

To report SUSPECTED ADVERSE REACTIONS, contact Braeburn at 1-833-274-9234 or FDA at 1-800-FDA-1088 or www.fda.gov/medwatch.

7 DRUG INTERACTIONS

- CYP3A4 Inhibitors and Inducers: Monitor patients starting or ending CYP3A4 inhibitors or inducers for potential over or under dosing. (7)
- Serotonergic Drugs: If concomitant use is warranted, monitor for serotonin syndrome, particularly during treatment initiation, and during dose adjustment of the serotonergic drug. (7)

8 USE IN SPECIFIC POPULATIONS

- Lactation: Buprenorphine passes into the mother's milk. (8.2)
- Geriatric Patients: Monitor for sedation or respiratory depression. (8.5)
- Moderate to Severe Hepatic Impairment: Not recommended. (5.14, 8.6)

FULL PRESCRIBING INFORMATION

WARNING: RISK OF SERIOUS HARM OR DEATH WITH INTRAVENOUS ADMINISTRATION; BRIXADI RISK EVALUATION AND MITIGATION STRATEGY

- Serious harm or death could result if administered intravenously. BRIXADI forms a liquid crystalline gel upon contact with body fluids and may cause occlusion, local tissue damage, and thrombo‐embolic events, including life-threatening pulmonary emboli, if administered intravenously. (5.1)
- Because of the risk of serious harm or death that could result from intravenous self‐administration, BRIXADI is only available through a restricted program called the BRIXADI REMS. Healthcare settings and pharmacies that order and dispense BRIXADI must be certified in this program and comply with the REMS requirements. (5.2)

1 INDICATIONS AND USAGE

BRIXADI is indicated for the treatment of moderate to severe opioid use disorder in patients who have initiated treatment with a single dose of a transmucosal buprenorphine product or who are already being treated with buprenorphine.

BRIXADI should be used as part of a complete treatment plan that includes counseling and psychosocial support.

2 DOSAGE AND ADMINISTRATION

2.1 Important Dosage and Administration Instructions

FOR SUBCUTANEOUS INJECTION ONLY. DO NOT ADMINISTER BRIXADI INTRAVENOUSLY, INTRAMUSCULARLY, OR INTRADERMALLY [see Warnings and Precautions (5.1), Instructions for Use (2.6)].

- BRIXADI exists in two formulations.
- Doses of BRIXADI (weekly) cannot be combined to yield a monthly dose.
- Only healthcare providers should prepare and administer BRIXADI.
- Administer BRIXADI as a single injection. Do not divide.
- BRIXADI should be injected slowly, into the subcutaneous tissue of the buttock, thigh, abdomen, or upper arm.
  - In patients who are not currently receiving buprenorphine treatment, for BRIXADI (weekly), the upper arm site should only be used after steady-state has been achieved (4 consecutive doses) [see Instructions for Use (2.6)]. Injection in the arm site was associated with approximately 10% lower plasma levels than other sites.
- Injection sites should be alternated/rotated between injections for BRIXADI (weekly) [see Instructions for Use (2.6)].
- For all patients, the dose of BRIXADI must be individualized based on patient tolerability and/or efficacy.
- BRIXADI (weekly) should be administered in 7-day intervals.
- BRIXADI (monthly) should be administered in 28-day intervals.
- For patients not currently receiving buprenorphine treatment, begin with a test dose of 4 mg transmucosal buprenorphine to establish that buprenorphine is tolerated without precipitated withdrawal, and then transition to BRIXADI (weekly). Initiating treatment with BRIXADI as the first buprenorphine product has not been studied. Initiating treatment with BRIXADI (monthly) in new entrants to treatment has not been studied [see Dosage and Administration (2.3)].
- Patients who are currently being treated with other buprenorphine-containing products can start treatment with either BRIXADI (weekly) or BRIXADI (monthly) [see Dosage and Administration (2.3)].
- Administer each injection using only the syringe and safety needle included with the product [see Instructions for Use (2.6)]. Caution: The BRIXADI needle cap is synthetically derived from natural rubber latex which may cause allergic reactions in latex-sensitive individuals [see Warnings and Precautions (5.10)].

To avoid missed doses, the weekly dose may be administered up to 2 days before or after the weekly time point, and the monthly dose may be administered up to 1 week before or after the monthly time point.

If a dose is missed, the next dose should be administered as soon as practically possible.

2.2 Patient Access to an Opioid Overdose Reversal Agent for the Emergency Treatment of Opioid Overdose

Inform patients and caregivers about opioid overdose reversal agents (e.g., naloxone, nalmefene) and discuss the importance of having access to an opioid overdose reversal agent. Because patients being treated for opioid use disorder have the potential for relapse, putting them at risk for opioid overdose, strongly consider prescribing or recommending an overdose reversal agent for the emergency treatment of opioid overdose, both when initiating and renewing treatment with BRIXADI. Also consider prescribing or recommending such an agent if the patient has household members (including children) or other close contacts at risk for accidental ingestion or opioid overdose [see Warnings and Precautions (5.4)].

Discuss the options for obtaining an opioid overdose reversal agent (e.g., prescription, over-the- counter, or as part of a community-based program) [see Warnings and Precautions (5.4)].

There are important differences among the opioid overdose reversal agents, such as route of administration, product strength, approved patient age range, and pharmacokinetics. Be familiar with these differences, as outlined in the approved labeling for those products, prior to recommending or prescribing such an agent.

Advise patients and caregivers that opioid overdose reversal agents, such as naloxone or nalmefene, may also be administered for a known or suspected overdose with buprenorphine itself. Higher than normal doses and repeated administration of an opioid overdose reversal agent may be necessary due to the long duration of action of buprenorphine and its affinity for the mu receptor [see Overdosage (10)].

2.3 Recommended Dosing

Patients Not Currently Receiving Buprenorphine Treatment

The recommended weekly dose in patients not currently receiving buprenorphine treatment is 24 mg of BRIXADI (weekly) titrated up over the first week of treatment as follows:

1. To avoid precipitating an opioid withdrawal syndrome, administer a test dose of transmucosal buprenorphine 4 mg when objective signs of mild to moderate withdrawal appear.
2. If the dose of transmucosal buprenorphine is tolerated without precipitated withdrawal, administer the first dose of BRIXADI (weekly), 16 mg.
3. Administer an additional dose of 8 mg BRIXADI (weekly) within 3 days of the first dose to achieve the recommended 24 mg BRIXADI (weekly) dose.

If needed, during this first week of treatment, administer an additional 8 mg dose of BRIXADI (weekly), waiting at least 24 hours after the previous injection, for a total weekly dose of 32 mg BRIXADI (weekly).

Administer subsequent BRIXADI (weekly) injections based on the total weekly dose that was established during Week One. Dosage adjustments can be made at weekly appointments with the maximum BRIXADI (weekly) dose being 32 mg.

A patient who misses a dose of BRIXADI (weekly) should receive the next dose as soon as possible. BRIXADI (weekly) should be administered in 7-day intervals.

Patients Switching from Transmucosal Buprenorphine-containing Products to BRIXADI

Patients currently being treated with a transmucosal buprenorphine-containing product may be switched directly to either BRIXADI (weekly) or BRIXADI (monthly).

Table 1 identifies the corresponding dose of BRIXADI when switching a patient from transmucosal buprenorphine to BRIXADI (weekly) or BRIXADI (monthly), expressing the transmucosal dose equivalents in terms of Subutex or Suboxone doses.

Table 1: Daily doses of sublingual buprenorphine (Subutex, Suboxone, or generic product equivalents) and suggested corresponding BRIXADI (weekly) or BRIXADI (monthly) doses
Daily dose of sublingual buprenorphine | BRIXADI (weekly) | BRIXADI (monthly)
≤ 6 mg | 8 mg | --
8-10 mg | 16 mg | 64 mg
12-16 mg | 24 mg | 96 mg
18-24 mg | 32 mg | 128 mg
Note: One SUBOXONE® (buprenorphine and naloxone) 8 mg/2 mg sublingual tablet provides equivalent buprenorphine exposure to one SUBUTEX® (buprenorphine HCl) 8 mg sublingual tablet or one Zubsolv® (buprenorphine and naloxone) 5.7 mg/1.4 mg sublingual tablet.

Patients Transitioning Between BRIXADI (weekly) and BRIXADI (monthly)

Patients may be transitioned from weekly to monthly or from monthly to weekly dosing of BRIXADI based on clinical judgment (see Table 2).

Table 2: Recommended dose when transitioning between BRIXADI (weekly) and BRIXADI (monthly)
BRIXADI (weekly) | BRIXADI (monthly)
16 mg | 64 mg
24 mg | 96 mg
32 mg | 128 mg

A patient who misses a dose of BRIXADI should receive the next dose as soon as possible. BRIXADI (weekly) should be administered in 7-day intervals. BRIXADI (monthly) should be administered in 28-day intervals.

Dose Adjustments of BRIXADI

An additional BRIXADI (weekly) 8 mg injection may be administered, based on clinical judgment during a dosing interval, up to a maximum dose of 32 mg per week of BRIXADI (weekly) or 128 mg per month of BRIXADI (monthly).

2.4 Patient Selection

Patients appropriate for BRIXADI (weekly) are:

1. adults who have tolerated a single 4 mg dose of a transmucosal buprenorphine-containing product. The test dose of transmucosal buprenorphine-containing product should be administered based on instructions in the appropriate product label.
2. adults who are currently being treated with a transmucosal buprenorphine-containing product.

Patients appropriate for BRIXADI (monthly) are adults who are currently being treated with a transmucosal buprenorphine-containing product. BRIXADI (monthly) is not intended for patients who are not currently receiving buprenorphine treatment.

2.5 Clinical Supervision

Periodic assessment is necessary to determine effectiveness of the treatment plan and overall patient progress. When evaluating the patient, examine the injection site for signs of infection or evidence of tampering or attempts to remove the depot.

Due to the chronic nature of opioid use disorder, the need for continuing medication-assisted treatment should be re-evaluated periodically. There is no maximum recommended duration of maintenance treatment. For some patients, treatment may continue indefinitely. If considering stopping treatment, the clinical status of the patient should be considered.

If BRIXADI is discontinued, its extended-release characteristics should be considered, and the patient should be monitored for several months for signs and symptoms of withdrawal and treated appropriately. After steady-state has been achieved, which is 4 weeks for BRIXADI (weekly) and 4 months for BRIXADI (monthly), patients discontinuing BRIXADI may have detectable plasma levels of buprenorphine for approximately 1 month for BRIXADI (weekly) and for approximately 4 months for BRIXADI (monthly). The correlation between plasma concentrations of buprenorphine and those detectable in urine is not known.

2.6 Instructions for Use

Prior to injecting BRIXADI, carefully read the instructions as well as the full prescribing information.

IMPORTANT INFORMATION:

- For subcutaneous injection only [see Warnings and Precautions (5.1)].
- To be prepared and administered by a healthcare provider only.
- Read the instructions carefully before handling the product.
- As a universal precaution, always wear gloves and inject BRIXADI under aseptic conditions.
- BRIXADI should be injected slowly, into the subcutaneous tissue of the buttock, thigh, abdomen, or upper arm.
- In patients who are not currently receiving buprenorphine treatment, for BRIXADI (weekly), the upper arm site should only be used after steady-state has been achieved (4 consecutive doses). Injection in the arm site was associated with approximately 10% lower plasma levels than other sites.
- Discard BRIXADI if the liquid contains visible particles or is cloudy. Discard BRIXADI after the expiration date shown on the carton or on the safety syringe label.

SAFETY SYRINGE PARTS (see Figures 1, 2, and 3 below)

Figure 1.

Figure 2.

Figure 3.

MATERIALS NEEDED FOR INJECTION
Illustrated in Figures 4.

- Alcohol wipe
- Cotton ball
- Sharps disposal container

Figure 4.

SELECTING AN INJECTION SITE
The areas for subcutaneous injection are highlighted in Figures 5. BRIXADI should not be administered to the same site of injection for at least 8 weeks for BRIXADI (weekly). No injection site rotation is required for BRIXADI (monthly).
BRIXADI should be injected slowly, into the subcutaneous tissue of the buttock, thigh, abdomen, or upper arm.
In patients who are not currently receiving buprenorphine treatment, for BRIXADI (weekly), the upper arm site should only be used after steady-state has been achieved (after 4 consecutive doses) [see Dosage and Administration (2.1)].

Figure 5.

PREPARE THE SAFETY SYRINGE
Step 1:
Wash hands thoroughly with soap and water prior to handling the safety syringe.
Step 2:
Remove the safety syringe components from the carton. Assemble the safety syringe. While holding the syringe guard body, insert the plunger into the body of the syringe and rotate clockwise until it is attached to the stopper inside the syringe as illustrated in Figures 6.

Figure 6.

Step 3:
Inspect the safety syringe closely:
Do not use the safety syringe after the expiration date shown on the carton or on the safety syringe label.

- The liquid should be clear and yellowish to yellow in color.
- A small air bubble may be visible.

Do not use the safety syringe if the liquid contains visible particles or is cloudy.

PREPARATION OF SITE
Step 4:

- Put on gloves.
- Clean the injection site with an alcohol wipe using a circular motion.

Do not touch the cleaned area again before injecting.

ADMINISTERING INJECTION
Step 5:

- Grasp the safety syringe by the syringe, as shown (see Figure 7).
- Carefully pull the needle cap straight off.
- Immediately dispose of the needle cap (Never try to recap the needle).

It is normal to see a small drop of liquid at the tip of the needle.

Figure 7.

Step 6:
Pinch the skin at the injection site between your thumb and index finger as shown in Figures 8.

Figure 8.

Step 7:
Hold the syringe, as shown, and insert the needle at an angle of approximately 90° (see Figure 9). The needle is designed to inject into the subcutaneous space. It is important to fully insert the needle.

Figure 9.

Step 8:

- After the needle is completely inserted into the subcutaneous tissue, release the skin that you are grasping. Slowly press down the plunger head until it latches in the safety device 'wings' (see Figure 10). This will ensure that all of the medication has been injected.
- Keep the plunger pressed fully down while you hold the safety syringe in place for an additional 2 seconds.

Figure 10.

Step 9:

- Gently pull the needle out of the skin.
- Keep the plunger fully depressed while you carefully lift the needle straight out from the injection site (see Figure 11).

Figure 11.

Step 10:

- As soon as you have completely removed the needle from the skin, slowly take your thumb off the plunger.
- Allow the syringe guard to automatically cover the exposed needle (see Figure 12).
- There may be a small amount of blood at the injection site. If needed, wipe with a cotton ball or gauze.

Figure 12.

DISPOSAL OF USED SAFETY SYRINGE
Step 11:
Put the used safety syringe immediately into a sharps container (see Figure 13).
POST INJECTION CARE

- Examine the injection site.
- If there is blood, press a cotton ball or gauze pad on the injection site.
- Do not rub the injection site.
- Apply an adhesive bandage if needed.
- Patient should be instructed to notify you immediately if excessive swelling, redness, heat or drainage develops at the injection site.

Figure 13.

2.7 Limits on Distribution

BRIXADI is subject to a risk evaluation and mitigation strategy (REMS) program that includes, among other elements, a restricted distribution program. The purpose of the restricted distribution program is to ensure that BRIXADI is only administered by a healthcare provider [see Warnings and Precautions (5.2)].

2.8 Removal of BRIXADI

BRIXADI forms a biodegradable liquid crystalline gel upon injection that is not always palpable and may not be conducive to surgical removal. Therefore, removal is not recommended.

3 DOSAGE FORMS AND STRENGTHS

BRIXADI is a sterile, yellowish to yellow-clear liquid solution and is provided as two different formulations, one for weekly and one for monthly administration in pre-filled, single-dose, syringes, with 23 gauge ½ inch needles, available in the following dosage strengths.

Table 3: BRIXADI (weekly) Strengths
BRIXADI (weekly) 50 mg/mL buprenorphine
Dosage Strength | Dosage Volume
8 mg | 0.16 mL
16 mg | 0.32 mL
24 mg | 0.48 mL
32 mg | 0.64 mL

Table 4: BRIXADI (monthly) Strengths
BRIXADI (monthly) 356 mg/mL buprenorphine
Dosage Strength | Dosage Volume
64 mg | 0.18 mL
96 mg | 0.27 mL
128 mg | 0.36 mL

4 CONTRAINDICATIONS

BRIXADI is contraindicated in patients with hypersensitivity (e.g., anaphylactic shock) to buprenorphine, or any other ingredients in the solution for injection [see Warnings and Precautions (5.10)].

5 WARNINGS AND PRECAUTIONS

5.1 Risk of Serious Harm or Death with Intravenous Administration

Intravenous injection presents significant risk of serious harm or death as BRIXADI forms a liquid crystalline gel upon contact with body fluids. Occlusion, local tissue damage, and thrombo-embolic events, including life-threatening pulmonary emboli, could result if administered intravenously [see Warnings and Precautions (5.2), Drug Abuse and Dependence (9.2)]. Do not administer intravenously, intramuscularly, or intradermally.

5.2 BRIXADI Risk Evaluation and Mitigation Strategy (REMS)

BRIXADI is available only through a restricted program called the BRIXADI REMS because of the risk of serious harm or death that could result from intravenous self-administration. The goal of the REMS is to mitigate serious harm or death that could result from intravenous self-administration by ensuring that healthcare settings and pharmacies are certified and only dispense BRIXADI directly to a healthcare provider for administration by a healthcare provider.

Notable requirements of the BRIXADI REMS include the following:

- Healthcare Settings and Pharmacies that order and dispense BRIXADI must be certified in the BRIXADI REMS.
- Certified Healthcare Settings and Pharmacies must establish processes and procedures to verify BRIXADI is provided directly to a healthcare provider for administration by a healthcare provider, and the drug is not dispensed to the patient.
- Certified Healthcare Settings and Pharmacies must not distribute, transfer, loan, or sell BRIXADI.

Further information is available at www.BRIXADIREMS.com or by calling 1-833-274-9234.

5.3 Addiction, Abuse, and Misuse

BRIXADI contains buprenorphine, a Schedule III controlled substance that can be abused in a manner similar to other opioids. Buprenorphine is sought by people with opioid use disorder and is subject to criminal diversion. Monitor all patients for progression of opioid use disorder and addictive behaviors [see Drug Abuse and Dependence (9.2)].

5.4 Life-Threatening Respiratory and Central Nervous System (CNS) Depression

Buprenorphine has been associated with life-threatening respiratory depression and death. Many, but not all, postmarketing reports regarding coma and death involved misuse by self-injection or were associated with the concomitant use of buprenorphine and benzodiazepines or other CNS depressant drugs including alcohol. Warn patients of the potential danger of self-administration of benzodiazepines or other CNS depressants while under treatment with BRIXADI [see Drug Interactions (7), Warnings and Precautions (5.5), Patient Counseling Information (17)].

Use BRIXADI with caution in patients with compromised respiratory function (e.g., chronic obstructive pulmonary disease, cor pulmonale, decreased respiratory reserve, hypoxia, hypercapnia, or pre-existing respiratory depression).

Due to its extended-release characteristics, if BRIXADI is discontinued as a result of compromised respiratory function, monitor patients for ongoing buprenorphine effects for approximately 1 month for BRIXADI (weekly) and for approximately 4 months for BRIXADI (monthly).

Educate patients and caregivers on how to recognize respiratory depression and emphasize the importance of calling 911 or getting emergency medical help right away in the event of a known or suspected overdose [see Patient Counseling Information (17)].

Opioids can cause sleep-related breathing disorders including central sleep apnea (CSA) and sleep related hypoxemia. Opioid use increases the risk of CSA in a dose-dependent fashion. In patients who present with CSA, monitor patient during treatment and consider dose reduction using best practices for opioid taper. [see Clinical Supervision (2.5)].

Patient Access to an Opioid Overdose Reversal Agent for the Emergency Treatment of Opioid Overdose

Inform patients and caregivers about opioid overdose reversal agents (e.g., naloxone, nalmefene) and discuss the importance of having access to an opioid overdose reversal agent.

Because patients being treated for opioid use disorder have the potential for relapse, putting them at risk for opioid overdose, strongly consider prescribing or recommending an opioid overdose reversal agent for the emergency treatment of an opioid overdose, both when initiating and renewing treatment with BRIXADI. Also consider prescribing or recommending such an agent if the patient has household members (including children) or other close contacts at risk for accidental ingestion or opioid overdose [see Dosage and Administration (2.2)].

Discuss the options for obtaining an opioid overdose reversal agent (e.g., prescription, over-the- counter, or as part of a community-based program).

There are important differences among the opioid overdose reversal agents, such as route of administration, product strength, approved patient age range, and pharmacokinetics. Be familiar with these differences, as outlined in the approved labeling for those products, prior to recommending or prescribing such an agent.

Advise patients and caregivers that an opioid overdose reversal agent, such as naloxone or nalmefene, may also be administered for a known or suspected overdose with buprenorphine itself. Higher than normal doses and repeated administration of an opioid overdose reversal agent may be necessary due to the long duration of action of buprenorphine and its affinity for the mu receptor [see Overdosage (10)].

Educate patients and caregivers on how to recognize respiratory depression and how to use an opioid overdose reversal agent for the emergency treatment of opioid overdose. Emphasize the importance of calling 911 or getting emergency medical help, even if an opioid overdose reversal agent is administered.

5.5 Managing Risks From Concomitant Use of Benzodiazepines or Other CNS Depressants

Concomitant use of buprenorphine and benzodiazepines and/or other CNS depressants (e.g., alcohol, non-benzodiazepine sedative/hypnotics, anxiolytics, tranquilizers, muscle relaxants, general anesthetics, antipsychotics, gabapentinoids [gabapentin or pregabalin], and other opioids) increases the risk of adverse reactions including overdose, respiratory depression, and death. Medication-assisted treatment of opioid use disorder, however, should not be categorically denied to patients taking these drugs. Prohibiting or creating barriers to treatment can pose an even greater risk of morbidity and mortality due to the opioid use disorder alone.

As a routine part of orientation to buprenorphine treatment, educate patients about the risks of concomitant use of benzodiazepines sedatives, opioid analgesics, and alcohol.

Develop strategies to manage use of prescribed or illicit benzodiazepines or other CNS depressants at initiation of buprenorphine treatment, or if it emerges as a concern during treatment. Adjustments to induction procedures and additional monitoring may be required. There is no evidence to support dose limitations or arbitrary caps of buprenorphine as a strategy to address benzodiazepine use in buprenorphine-treated patients. However, if a patient is sedated at the time of buprenorphine dosing, delay or omit the buprenorphine dose if appropriate.

Cessation of benzodiazepines or other CNS depressants is preferred in most cases of concomitant use with buprenorphine. In some cases, monitoring in a higher level of care for taper may be appropriate. In others, gradually tapering a patient off of a prescribed benzodiazepine or other CNS depressant or decreasing to the lowest effective dose may be appropriate.

For patients in buprenorphine treatment, benzodiazepines are not the treatment of choice for anxiety or insomnia. Before co-prescribing benzodiazepines, ensure that patients are appropriately diagnosed and consider alternative medications and non-pharmacologic treatments to address anxiety or insomnia. Ensure that other healthcare providers prescribing benzodiazepines or other CNS depressants are aware of the patients' buprenorphine treatment and coordinate care to minimize the risks associated with concomitant use.

If concomitant use is warranted, strongly consider recommending or prescribing an opioid overdose reversal agent, as is recommended for all patients on buprenorphine treatment for opioid use disorder [see Dosage and Administration (2.2), Warnings and Precautions (5.4), Overdosage (10)].

In addition, take measures to confirm that patients are taking their medications as prescribed and are not diverting or supplementing with illicit drugs. Toxicology screening should test for prescribed and illicit benzodiazepines [see Drug Interactions (7)].

5.6 Neonatal Opioid Withdrawal Syndrome

Neonatal opioid withdrawal syndrome (NOWS) is an expected and treatable outcome of prolonged use of opioids during pregnancy, whether that use is medically-authorized or illicit. Unlike opioid withdrawal syndrome in adults, NOWS may be life-threatening if not recognized and treated in the neonate. Healthcare providers should observe newborns for signs of NOWS and manage accordingly [see Use in Specific Populations (8.1)].

Advise pregnant women receiving opioid addiction treatment with BRIXADI of the risk of neonatal opioid withdrawal syndrome and ensure that appropriate treatment will be available [see Use in Specific Populations (8.1)]. This risk must be balanced against the risk of untreated opioid addiction which often results in continued or relapsing illicit opioid use and is associated with poor pregnancy outcomes. Therefore, prescribers should discuss the importance and benefits of management of opioid addiction throughout pregnancy.

5.7 Adrenal Insufficiency

Cases of adrenal insufficiency have been reported with opioid use, more often following greater than one month of use. Presentation of adrenal insufficiency may include non-specific symptoms and signs including nausea, vomiting, anorexia, fatigue, weakness, dizziness, and low blood pressure. If adrenal insufficiency is suspected, confirm the diagnosis with diagnostic testing as soon as possible. If adrenal insufficiency is diagnosed, treat with physiologic replacement doses of corticosteroids. Wean the patient off of the opioid to allow adrenal function to recover and continue corticosteroid treatment until adrenal function recovers. Other opioids may be tried as some cases reported use of a different opioid without recurrence of adrenal insufficiency. The information available does not identify any particular opioids as being more likely to be associated with adrenal insufficiency.

5.8 Risk of Opioid Withdrawal with Abrupt Discontinuation of BRIXADI Treatment

Buprenorphine is a partial agonist at the mu-opioid receptor and chronic administration produces physical dependence of the opioid type, characterized by withdrawal signs and symptoms upon abrupt discontinuation or rapid taper. The withdrawal syndrome is milder than that seen with full agonists and may be delayed in onset [see Drug Abuse and Dependence (9.2, 9.3)].

Patients who elect to discontinue BRIXADI treatment should be monitored for withdrawal signs and symptoms with consideration given to the product's extended-release characteristics [See Clinical Pharmacology (12.3)].

Consider transmucosal buprenorphine if needed to treat withdrawal after discontinuing BRIXADI.

5.9 Risk of Hepatitis, Hepatic Events

Cases of cytolytic hepatitis and hepatitis with jaundice have been observed in individuals receiving buprenorphine for the treatment of opioid use disorder, both in clinical trials and through postmarketing adverse event reports.

The spectrum of abnormalities ranges from transient asymptomatic elevations in hepatic transaminases to case reports of death, hepatic failure, hepatic necrosis, hepatorenal syndrome, and hepatic encephalopathy. In many cases, the presence of pre-existing liver enzyme abnormalities, infection with hepatitis B or hepatitis C virus, concomitant usage of other potentially hepatotoxic drugs, and ongoing injection drug abuse may have played a causative or contributory role. In other cases, insufficient data were available to determine the etiology of the abnormality. Withdrawal of buprenorphine has resulted in amelioration of acute hepatitis in some cases; however, in other cases no dose reduction was necessary. The possibility exists that buprenorphine had a causative or contributory role in the development of the hepatic abnormality in some cases.

Liver function tests are recommended prior to initiation of treatment to establish a baseline. Periodic monitoring of liver function during treatment is also recommended. A biological and etiological evaluation is recommended when a hepatic event is suspected. Monitor patients with declining hepatic function for side effects resulting from increased exposure to buprenorphine.

5.10 Hypersensitivity Reactions

Cases of hypersensitivity to buprenorphine containing products have been reported both in clinical trials and in the postmarketing experience. Cases of bronchospasm, angioneurotic edema, and anaphylactic shock have been reported. The most common signs and symptoms include rashes, hives, and pruritus. A history of hypersensitivity to buprenorphine or other components is a contraindication to the use of BRIXADI [see Contraindications (4)].

Latex Allergies: The BRIXADI needle cap is synthetically derived from natural rubber latex which may cause allergic reactions in latex-sensitive individuals.

5.11 Precipitation of Opioid Withdrawal Signs and Symptoms

Because of the partial agonist properties of buprenorphine, BRIXADI injection may precipitate opioid withdrawal signs and symptoms in individuals physically dependent on full opioid agonists such as heroin, morphine, or methadone before the effects of the full opioid agonist have subsided.

In patients who are new entrants to treatment, administer a test dose of transmucosal buprenorphine and monitor for precipitated withdrawal and treat appropriately [see Dosage and Administration (2.3)].

5.12 Risks Associated with Treatment of Emergent Acute Pain

While on BRIXADI, situations may arise where patients need acute pain management, or may require anesthesia. Treat patients receiving BRIXADI with non-opioid analgesic whenever possible. Patients requiring opioid therapy for analgesia may be treated with a high-affinity full opioid analgesic under the supervision of a healthcare provider, with particular attention to respiratory function. Higher doses may be required for analgesic effect. Therefore, a higher potential for toxicity exists with opioid administration. If opioid therapy is required as part of anesthesia, patients should be continuously monitored in an anesthesia care setting by persons not involved in the conduct of the surgical or diagnostic procedure. The opioid therapy should be provided by individuals specifically trained in the use of anesthetic drugs and the management of the respiratory effects of potent opioids, specifically the establishment and maintenance of a patent airway and assisted ventilation.

Advise patients of the importance of instructing their family members, in the event of emergency, to inform the treating healthcare provider or emergency room staff that the patient is physically dependent on an opioid and that the patient is being treated with BRIXADI [see Patient Counseling Information (17)].

Please refer to Section 2.5 for further details on duration of exposure following discontinuation for both weekly and monthly BRIXADI formulations. [see Clinical Supervision (2.5)].

5.13 Use in Opioid Naïve Patients

There have been reported deaths of opioid naïve individuals who received a 2 mg dose of buprenorphine as a sublingual tablet. BRIXADI is not appropriate for use in opioid naïve patients.

5.14 Use in Patients With Impaired Hepatic Function

In a pharmacokinetic study with transmucosal buprenorphine, buprenorphine plasma levels were found to be higher and the half-life was found to be longer in subjects with moderate and severe hepatic impairment, but not in subjects with mild hepatic impairment. The effect of hepatic impairment on the pharmacokinetics of BRIXADI, has not been studied.

Because of the long-acting nature of the product, adjustments to dosages of BRIXADI are not rapidly reflected in plasma buprenorphine levels. Because buprenorphine levels cannot be rapidly decreased, patients with pre-existing moderate to severe hepatic impairment are not candidates for treatment with BRIXADI.

Patients who develop moderate to severe hepatic impairment while being treated with BRIXADI should be monitored for several months for signs and symptoms of toxicity or overdose caused by increased levels of buprenorphine and patients may require a dose adjustment [see Use in Specific Populations (8.6)].

5.15 QTc Prolongation

Thorough QT studies with buprenorphine products have demonstrated QT prolongation ≤ 15 msec. This QTc prolongation effect does not appear to be mediated by hERG channels. Based on these two findings, buprenorphine is unlikely to be pro-arrhythmic when used alone in patients without risk factors. The risk of combining buprenorphine with other QT- prolonging agents is not known.

Consider these observations in clinical decisions when prescribing BRIXADI to patients with risk factors such as hypokalemia, bradycardia, recent conversion from atrial fibrillation, congestive heart failure, digitalis therapy, baseline QT prolongation, subclinical long-QT syndrome, or severe hypomagnesemia. [see Clinical Pharmacology (12.2)].

5.16 Impairment of Ability to Drive and Operate Machinery

BRIXADI may impair the mental or physical abilities required for the performance of potentially dangerous tasks such as driving a car or operating machinery, especially for the first few days following treatment and dose adjustment. Buprenorphine plasma levels accumulate during the BRIXADI (weekly) or BRIXADI (monthly) injections, which achieves steady-state at the fourth weekly or monthly injection. Caution patients about driving or operating hazardous machinery until they are reasonably certain that BRIXADI does not adversely affect their ability to engage in such activities. [see Clinical Pharmacology (12.3)].

5.17 Orthostatic Hypotension

Buprenorphine may produce orthostatic hypotension in ambulatory patients.

5.18 Elevation of Cerebrospinal Fluid Pressure

Buprenorphine may elevate cerebrospinal fluid pressure and should be used with caution in patients with head injury, intracranial lesions, and other circumstances where cerebrospinal pressure may be increased. Buprenorphine can produce miosis and changes in the level of consciousness that may interfere with patient evaluation.

5.19 Elevation of Intracholedochal Pressure

Buprenorphine has been shown to increase intracholedochal pressure, as do other opioids, and thus should be administered with caution to patients with dysfunction of the biliary tract.

5.20 Effects in Acute Abdominal Conditions

Buprenorphine may obscure the diagnosis or clinical course of patients with acute abdominal conditions.

5.21 Unintentional Pediatric Exposure

Buprenorphine can cause severe, possibly fatal, respiratory depression in children who are accidentally exposed to it.

6 ADVERSE REACTIONS

The following adverse reactions are discussed in more detail in other sections of the labeling:

- Addiction, Abuse, and Misuse [see Warnings and Precautions (5.3)]
- Respiratory and CNS Depression [see Warnings and Precautions (5.4)]
- Neonatal Opioid Withdrawal Syndrome [see Warnings and Precautions (5.6)]
- Adrenal Insufficiency [see Warnings and Precautions (5.7)]
- Opioid Withdrawal [see Warnings and Precautions (5.8, 5.11)]
- Hepatitis, Hepatic Events [see Warnings and Precautions (5.9)]
- Hypersensitivity Reactions [see Warnings and Precautions (5.10)]
- Orthostatic Hypotension [see Warnings and Precautions (5.17)]
- Elevation of Cerebrospinal Fluid Pressure [see Warnings and Precautions (5.18)]
- Elevation of Intracholedochal Pressure [see Warnings and Precautions (5.19)]

6.1 Clinical Trials Experience

Because clinical trials are conducted under widely varying conditions, adverse reaction rates observed in the clinical trials of a drug cannot be directly compared to rates in the clinical trials of another drug and may not reflect the rates observed in practice.

The safety of BRIXADI was evaluated in 440 opioid-dependent patients across two, Phase 3 clinical studies: one double-blind, active-control (n=213) and one open-label (n=227). In these studies, a total of 305 patients were exposed to BRIXADI for at least 24 weeks and 132 patients were exposed for at least 48 weeks.

In the first 12-week phase of the double-blind, double-dummy, active-controlled study, patients received BRIXADI (weekly) (16, 24, 32 mg) or matching placebo injections after a one-week titration. In the second 12-week phase of the study, patients remaining in the study received BRIXADI (monthly) (64, 96, 128, or 160 mg) or matching placebo injections. The 160 mg monthly dose is not an approved dose. Those randomized to receiving placebo injections were the active control groups and received sublingual buprenorphine/naloxone tablets at corresponding doses to BRIXADI. Patients receiving active BRIXADI injections also received placebo sublingual tablets.

Adverse reactions led to premature discontinuation in 10 (4.7%) patients in the group receiving BRIXADI compared to 5 (2.3%) patients in the sublingual buprenorphine/naloxone group, during the double-blind study.

Adverse reactions commonly reported after BRIXADI administration (≥5%, regardless of dose and regimen) in the double-blind study, were injection site pain (9.9%), headache (7.5%), constipation (7.5%), nausea (7.0%), injection site erythema (6.6%), injection site pruritus (6.1%), Insomnia (5.6%), and urinary tract infection (5.2%).

Table 5 shows the adverse reactions for BRIXADI compared with the active-control group (SL BPN/NX) in the double-blind study.

Table 5: Adverse Reactions in the Phase 3 Double-Blind Study: ≥ 2% of Patients Receiving BRIXADI (Excluding Injection Site Reactions).
System Organ Class (SOC) | BRIXADI Total [= This group includes all subjects exposed to varying doses of both the BRIXADI (weekly) and BRIXADI (monthly) formulations.] | SL BPN/NX [= SL BPN/NX denotes the active comparator: patients assigned to daily buprenorphine with sham (placebo) injections. Patients randomized to this group could also receive a 'booster' injection of BRIXADI (weekly), 8mg, per protocol. All patients in Study 421 received a single test dose of 4mg SL BPN/NX before randomization into either arm.]
Preferred Term (PT) [= report of adverse reactions that occurred in ≥ 2% of the patients randomized to BRIXADI in Study HS-11-421. Patients are represented once per PT] | (N=213) n(%) | (N=215) n(%)
Cardiac disorders | 6 (2.8%) | 9 (4.2%)
Tachycardia | 5 (2.3) | 5 (2.3)
Gastrointestinal disorders | 43 (20.2%) | 45 (20.9%)
Constipation | 16 (7.5) | 16 (7.4)
Diarrhea | 6 (2.8) | 7 (3.3)
Nausea | 15 (7.0) | 17 (7.9)
Vomiting | 9 (4.2) | 8 (3.7)
Infections and infestations | 42 (19.7%) | 50 (23.3%)
Urinary tract infection | 11 (5.2) | 10 (4.7)
Upper respiratory tract infection | 9 (4.2) | 9 (4.2)
Musculoskeletal and connective tissue disorders | 20 (9.4%) | 22 (10.2%)
Arthralgia | 7 (3.3) | 3 (1.4)
Nervous system disorders | 27 (12.7%) | 27 (12.6%)
Headache | 16 (7.5) | 17 (7.9)
Psychiatric disorders | 20 (9.4%) | 20 (9.3%)
Anxiety | 6 (2.8) | 7 (3.3)
Insomnia | 12 (5.6) | 6 (2.8)

Injection site reactions in the double-blind study are presented in Table 6 below. The majority of injection site-related adverse events were mild or moderate in severity. No injection site reactions were reported as severe intensity.

Table 6: Injection site reactions in the Double-Blind Phase 3 Study: ≥ 2% of Patients Receiving BRIXADI
Preferred Term (PT) [= Injection site reactions (ISR) that occurred in ≥2% of patients receiving BRIXADI, in the controlled trial, HS-11-421. Patients are represented once per PT.] | BRIXADI Total [= This group includes patients exposed to varying doses of both the BRIXADI weekly and monthly formulations.] (N=213) n(%) | SL BPN/NX [= SL BPN/NX denotes the active comparator: subjects assigned to daily buprenorphine with sham (placebo) injections. Patients randomized to this group could also receive a supplemental 'booster' injection of BRIXADI (weekly), 8mg, per protocol.] (N=215) n(%)
Administration site reactions [= The ISRs that occurred in ≥2% of the patients randomized to BRIXADI were reported under the HGLT of Administration site reactions. However, ISRs were also identified under the Bacterial infectious disorders HGLT (of which, there were three injection site related cellulitis reactions in the BRIXADI group and one in the SL BPN/NX group, respectively) but those numbers did not rise to level of reporting. Tabulation included all events coded as treatment emergent and injection site reactions, regardless of treatment emergent flags.] | 44 (20.7%) | 49 (22.8%)
Injection site pain | 21 (9.9%) | 17 (7.9%)
Injection site erythema | 14 (6.6%) | 12 (5.6%)
Injection site pruritus | 13 (6.1%) | 13 (6.0%)
Injection site swelling | 10 (4.7%) | 7 (3.3%)
Injection site reaction | 9 (4.2%) | 7 (3.3%)

6.2 Postmarketing Experience

The following adverse reactions have been identified during post-approval use of buprenorphine. Because these reactions are reported voluntarily from a population of uncertain size, it is not always possible to reliably estimate their frequency or establish a causal relationship to drug exposure.

The most frequently reported postmarketing adverse event observed with buprenorphine sublingual tablets, excluding drug exposure during pregnancy, was drug misuse or abuse.

Serotonin syndrome: Cases of serotonin syndrome, a potentially life-threatening condition, have been reported during concomitant use of opioids with serotonergic drugs.

Adrenal insufficiency: Cases of adrenal insufficiency have been reported with opioid use, more often following greater than one month of use.

Anaphylaxis: Anaphylaxis has been reported with buprenorphine [see Contraindications (4)].

Androgen deficiency: Cases of androgen deficiency have occurred with chronic use of opioids [see Clinical Pharmacology (12.2)].

The following adverse reactions have been identified during post-approval use of an identical buprenorphine extended-release injection for subcutaneous use outside of the United States and are not described elsewhere in the label. Because these reactions are reported voluntarily from a population of uncertain size, it is not always possible to reliably estimate their frequency or establish a causal relationship to drug exposure.

Injection site mass, abscess, ulceration, and necrosis: Cases of injection site abscess, ulceration and necrosis have been reported after treatment initiation. Some cases have required debridement and antibiotic treatment. The likelihood of serious injection site reactions may be increased with inadvertent intramuscular or intradermal administration.

Insufficient dosing: Cases of drug withdrawal reactions consistent with insufficient drug dosing have been reported, often occurring at or after two weeks of treatment initiation and resolving upon dose increase.

Hypoglycemia: Cases of hypoglycemia have been reported in patients taking opiods. Most reports were in patients with at least one predisposing risk factor (e.g., diabetes).

Opioid-induced esophageal dysfunction (OIED): Cases of OIED have been reported in patients taking opioids, and may occur more frequently in patients taking higher doses of opioids, and/or in patients taking opioids longer term.

7 DRUG INTERACTIONS

Table 7: Clinically Significant Drug Interactions
Benzodiazepines and other Central Nervous System (CNS) Depressants
Clinical Impact: | Due to additive pharmacologic effects, the concomitant use of benzodiazepines or other CNS depressants, including alcohol, increases the risk of respiratory depression, profound sedation, coma, and death.
Intervention: | Cessation of benzodiazepines or other CNS depressants is preferred in most cases of concomitant use. In some cases, monitoring in a higher level of care for taper may be appropriate. In others, gradually tapering a patient off a prescribed benzodiazepine or CNS depressant or decreasing to the lowest effective dose may be appropriate. Similarly, cessation of other CNS depressants is preferred when possible. Before co-prescribing benzodiazepines for anxiety or insomnia, ensure that patients are appropriately diagnosed and consider alternative medications and non-pharmacologic treatment [see Warnings and Precautions (5.5)]. If concomitant use is warranted, strongly consider recommending or prescribing an opioid overdose reversal agent, as is recommended for all patients on buprenorphine treatment for opioid use disorder [see Warnings and Precautions (5.4)].
Examples: | Alcohol, non-benzodiazepine sedatives/hypnotics, anxiolytics, tranquilizers, muscle relaxants, general anesthetics, antipsychotics, gabapentinoids (gabapentin or pregabalin), and other opioids.
Inhibitors of CYP3A4
Clinical Impact: | The effects on buprenorphine exposure in patients treated with BRIXADI have not been studied, and the effects may be dependent on the route of administration. Buprenorphine is metabolized to norbuprenorphine primarily by CYP3A4; therefore, potential interactions may occur when BRIXADI is given concurrently with agents that affect CYP3A4 activity [see Clinical Pharmacology (12.3)]. The concomitant use of buprenorphine and CYP3A4 inhibitors can increase the plasma concentration of buprenorphine, resulting in increased or prolonged opioid effects, particularly when an inhibitor is added after a stable dose of BRIXADI is achieved.
Intervention: | Patients Converted to BRIXADI Treatment from a Regimen of Transmucosal Buprenorphine used Concomitantly with CYP3A4 Inhibitors: Monitor to ensure that the plasma buprenorphine level provided by BRIXADI is adequate. Patients Already on BRIXADI who Require Newly-Initiated Treatment with a CYP3A4 Inhibitor: Monitor for signs and symptoms of over-medication. If signs and symptoms of buprenorphine toxicity or overdose occur but the concomitant medication cannot be reduced or discontinued, reduce the dose of BRIXADI. If available doses do not permit achievement of the desired dose, it may be necessary to discontinue treatment with BRIXADI and treat the patient with a formulation of buprenorphine that permits more precise dose adjustments. Patients Stabilized on BRIXADI in the Setting of Concomitant Medication That is a CYP3A4 Inhibitor, and the Concomitant Medication is Discontinued: Monitor for withdrawal and consider a dosage adjustment of BRIXADI. If the dose of BRIXADI cannot be adjusted to an adequate level in the absence of the concomitant medication, transition the patient back to a formulation of buprenorphine that permits more precise dose adjustments.
Examples: | azole antifungals (e.g., ketoconazole), macrolide antibiotics (e.g., erythromycin), and protease inhibitors (e.g., ritonavir, indinavir, and saquinavir)
CYP3A4 Inducers
Clinical Impact: | The effects of co-administered CYP3A4 inducers on buprenorphine exposure in patients treated with BRIXADI have not been studied. Buprenorphine is metabolized to norbuprenorphine primarily by CYP3A4; therefore, potential interactions may occur when BRIXADI is given concurrently with agents that affect CYP3A4 activity [see Clinical Pharmacology (12.3)]. CYP3A4 inducers may induce metabolism of buprenorphine and, therefore, may cause increased clearance of the drug which could lead to a decrease in buprenorphine plasma concentrations, lack of efficacy or, possibly, development of an abstinence syndrome.
Intervention: | Patients Converted to BRIXADI Treatment from a Regimen of Transmucosal Buprenorphine used Concomitantly with CYP3A4 Inducers: Monitor to ensure that the plasma buprenorphine level provided by BRIXADI is adequate. Patients Already on BRIXADI who Require Newly-Initiated Treatment with a CYP3A4 Inducer: Monitor for withdrawal. If the dose of BRIXADI is not adequate in the presence of the concomitant medication, and the concomitant medication cannot be reduced or discontinued, adjust the dose of BRIXADI. If the dose of BRIXADI cannot be adjusted to an adequate level, transition the patient back to a formulation of buprenorphine that permits more precise dose adjustments. Patients Stabilized on BRIXADI in the setting of Concomitant Medication that is a CYP3A4 Inducer, and the Concomitant Medication is Discontinued: Monitor for signs and symptoms of over-medication. If the dose provided by BRIXADI is excessive in the absence of the concomitant inducer, consider reducing the dose of BRIXADI. If the dose of BRIXADI cannot be adjusted to an adequate level, transition the patient back to a formulation of buprenorphine that permits more precise dose adjustments [see Clinical Pharmacology (12.3)].
Examples: | Rifampin, carbamazepine, phenytoin, phenobarbital
Antiretrovirals: Non-nucleoside reverse transcriptase inhibitors (NNRTIs)
Clinical Impact: | Non-nucleoside reverse transcriptase inhibitors (NNRTIs) are metabolized principally by CYP3A4. Efavirenz, nevirapine, and etravirine are known CYP3A4 inducers, whereas delaviridine is a CYP3A4 inhibitor. Significant pharmacokinetic interactions between NNRTIs (e.g., efavirenz and delviradine) and buprenorphine have been shown in clinical studies, but these pharmacokinetic interactions did not result in any significant pharmacodynamics effects.
Intervention: | It is recommended that patients who are on BRIXADI treatment have their dose monitored for increase or decrease in therapeutic effects if NNRTIs are added to their treatment regimen.
Examples: | Efavirenz, nevirapine, etravirine, delavirdine
Antiretrovirals: Protease Inhibitors (PIs)
Clinical Impact: | Studies have shown some antiretroviral protease inhibitors (PIs) with CYP3A4 inhibitory activity (e.g., nelfinavir, lopinavir/ritonavir, ritonavir) have little effect on buprenorphine pharmacokinetics and no significant pharmacodynamics effects. Other PIs with CYP3A4 inhibitory activity (e.g., atazanavir and atazanavir/ritonavir) resulted in elevated levels of buprenorphine and norbuprenorphine and patients in one study reported increased sedation. Symptoms of opioid excess have been found in postmarketing reports of patients receiving buprenorphine and atazanavir with and without ritonavir concomitantly.
Intervention: | If treatment with atazanavir with and without ritonavir must be initiated in a patient already treated with BRIXADI, the patient should be monitored for signs and symptoms of over-medication. It may be necessary to discontinue treatment with BRIXADI and treat the patient with a sublingual buprenorphine product that permits rapid dose adjustments.
Examples: | Atazanavir, ritonavir
Antiretrovirals: Nucleoside reverse transcriptase inhibitors (NRTIs)
Clinical impact: | Nucleoside reverse transcriptase inhibitors (NRTIs) do not appear to induce or inhibit the P450 enzyme pathway, thus no interactions with buprenorphine are expected.
Intervention: | None
Serotonergic Drugs
Clinical Impact: | The concomitant use of opioids with other drugs that affect the serotonergic neurotransmitter system has resulted in serotonin syndrome.
Intervention: | If concomitant use is warranted, carefully observe the patient, particularly during treatment initiation, and during dose adjustment of the serotonergic drug. Discontinue BRIXADI if serotonin syndrome is suspected.
Examples: | Selective serotonin reuptake inhibitors (SSRIs), serotonin and norepinephrine reuptake inhibitors (SNRIs), tricyclic antidepressants (TCAs), triptans, S-HT3 receptor antagonists, drugs that affect serotonin neurotransmitter system (e.g., mirtazapine, trazodone, tramadol), certain muscle relaxants (i.e. cyclobenzaprine, metaxalone), and monoamine oxidase (MAO) inhibitors (those intended to treat psychiatric disorders and also others, such as linezolid and intravenous methylene blue).
Monomaine Oxidase Inhibitors (MAOIs)
Clinical Impact: | MAOI interactions with opioids may manifest as serotonin syndrome or opioid toxicity (e.g., respiratory depression, coma).
Intervention: | The use of BRIXADI is not recommended for patients taking MAOIs or within 14 days of stopping such treatment.
Examples: | Phenelzine, tranylcypromine, linezolid
Muscle Relaxants
Clinical Impact: | Buprenorphine may enhance the neuromuscular blocking action of skeletal muscle relaxants and produce an increased degree of respiratory depression.
Intervention: | Monitor patients receiving muscle relaxants and BRIXADI for signs of respiratory depression that may be greater than otherwise expected and decrease the dosage of the muscle relaxant as necessary. Due to the risk of respiratory depression with concomitant use of skeletal muscle relaxants and opioids, strongly consider recommending or prescribing an opioid overdose reversal agent, as is recommended for all patients on buprenorphine treatment for opioid use disorder. [see Dosage and Administration (2.2), Warnings and Precautions (5.4, 5.5)].
Examples: | Cyclobenzaprine, metaxolone
Diuretics
Clinical Impact: | Opioids can reduce the efficacy of diuretics by inducing the release of antidiuretic hormone.
Intervention: | Monitor patients for signs of diminished diuresis and/or effects on blood pressure and increase the dosage of the diuretic needed.
Anticholinergic Drugs
Clinical Impact: | The concomitant use of anticholinergic drugs may increase the risk of urinary retention and/or severe constipation, which may lead to paralytic ileus.
Intervention: | Monitor patients for signs of urinary retention or reduced gastric motility when BRIXADI is used concomitantly with anticholinergic drugs.

8 USE IN SPECIFIC POPULATIONS

8.1 Pregnancy

Risk Summary

The data on use of buprenorphine, the active ingredient in BRIXADI in pregnancy, are limited; however, these data do not indicate an increased risk of major malformations specifically due to buprenorphine exposure. There are limited data from randomized clinical trials in women maintained on sublingual buprenorphine that were not designed appropriately to assess the risk of major malformations [see Data].

Embryofetal death was observed in both rats and rabbits administered buprenorphine during the period of organogenesis at doses 21 times and equal to, respectively, the mean daily dose of 4.6 mg buprenorphine delivered by either 32 mg BRIXADI (weekly) or 128 mg BRIXADI (monthly). Pre- and post-natal development studies in rats demonstrated increased neonatal deaths at doses approximately equal to and above and dystocia at 11 times the mean daily dose of 4.6 mg buprenorphine. No clear teratogenic effects were seen when buprenorphine was administered during organogenesis with a range of doses 4 times and greater than the mean daily dose of 4.6 mg of buprenorphine. However, increases in skeletal abnormalities were noted in rats and rabbits administered buprenorphine daily during organogenesis at doses 2 and 21 times the mean daily dose of 4.6 mg of buprenorphine, respectively. In a few studies, some events such as acephalus and omphalocele were also observed but these findings were not clearly treatment-related [see Data]. Based on animal data, advise pregnant women of the potential risk to a fetus.

The estimated background risk of major birth defects and miscarriage for the indicated population are unknown. In the U.S. general population, the estimated background risk of major birth defects and miscarriage in clinically recognized pregnancies is 2-4% and 15-20%, respectively.

BRIXADI should be used during pregnancy only if the potential benefit justifies the potential risk to the fetus

Clinical Considerations

Disease-associated maternal and embryo-fetal risk

Untreated opioid addiction in pregnancy is associated with adverse obstetrical outcomes such as low birth weight, preterm birth, and fetal death. In addition, untreated opioid addiction often results in continued or relapsing illicit opioid use.

Dose Adjustment during Pregnancy and the Postpartum Period

Dosage adjustments of buprenorphine may be required during pregnancy, even if the patient was maintained on a stable dose prior to pregnancy. Withdrawal signs and symptoms should be monitored closely, and the dose adjusted as necessary.

Fetal/neonatal adverse reactions

Neonatal opioid withdrawal syndrome may occur in newborn infants of mothers who are receiving treatment with BRIXADI.

Neonatal opioid withdrawal syndrome presents as irritability, hyperactivity, and abnormal sleep pattern, high pitched cry, tremor, vomiting, diarrhea, and/or failure to gain weight. Signs of neonatal withdrawal usually occur in the first days after birth. The duration and severity of neonatal opioid withdrawal syndrome may vary. Observe newborns for signs of neonatal opioid withdrawal syndrome and manage accordingly [see Warnings and Precautions (5.6)].

Labor or Delivery

Opioid-dependent women on buprenorphine maintenance therapy may require additional analgesia during labor.

As with all opioids, use of buprenorphine prior to delivery may result in respiratory depression in the newborn. Closely monitor neonates for signs of respiratory depression. An opioid antagonist such as naloxone or nalmefene, should be available for reversal of opioid induced respiratory depression in the neonate.

Data

Human Data

Studies have been conducted to evaluate neonatal outcomes in women exposed to buprenorphine during pregnancy. Limited data from trials, observational studies, case series, and case reports on buprenorphine use in pregnancy do not indicate an increased risk of major malformations specifically due to buprenorphine. Several factors may complicate the interpretation of investigations of the children of women who take buprenorphine during pregnancy, including maternal use of illicit drugs, late presentation for prenatal care, infection, poor compliance, poor nutrition, and psychosocial circumstances. Interpretation of data is complicated further by the lack of information on untreated opioid-dependent pregnant women, who would be the most appropriate group for comparison. Rather, women on another form of opioid medication-assisted treatment, or women in the general population are generally used as the comparison group. However, women in these comparison groups may be different from women prescribed buprenorphine-containing products with respect to maternal factors that may lead to poor pregnancy outcomes.

In a multicenter, double-blind, randomized, controlled trial (Maternal Opioid Treatment: Human Experimental Research [MOTHER]) designed primarily to assess neonatal opioid withdrawal effects, opioid-dependent pregnant women were randomized to buprenorphine (n=86) or methadone (n=89) treatment, with enrollment at an average gestational age of 18.7 weeks in both groups. A total of 28 of the 86 women in the buprenorphine group (33%) and 16 of the 89 women in the methadone group (18%) discontinued treatment before the end of pregnancy.

Among women who remained in treatment until delivery, there was no difference between buprenorphine-treated and methadone-treated groups in the number of neonates requiring NOWS treatment or in the peak severity of NOWS. Buprenorphine-exposed neonates required less morphine (mean total dose, 1.1 mg vs 10.4 mg), had shorter hospital stays (10.0 days vs 17.5 days), and shorter duration of treatment for NOWS (4.1 days vs 9.9 days) compared to the methadone-exposed group. There were no differences between groups in other primary outcomes (neonatal head circumference) or secondary outcomes (weight and length at birth, preterm birth, gestational age at delivery, and 1-minute and 5-minute Apgar scores), or in the rates of maternal or neonatal adverse events. The outcomes among mothers who discontinued treatment before delivery and may have relapsed to illicit opioid use are not known. Because of the imbalance in discontinuation rates between the buprenorphine and methadone groups, the study findings are difficult to interpret.

Animal Data

The exposure margins below are based on the mean daily dose of 4.6 mg buprenorphine delivered by 32 mg BRIXADI (weekly) or 128 mg BRIXADI (monthly) on body surface area comparisons, unless otherwise noted.

No definitive drug-related teratogenic effects were observed in rats and rabbits at IM doses up to 30 mg/kg/day (64 times and 127 times, respectively, on a mg/m^2 basis). Maternal toxicity resulting in mortality was noted in these studies in both rats and rabbits. Acephalus was observed in one rabbit fetus from the low-dose group and omphalocele was observed in two rabbit fetuses from the same litter in the mid-dose group; no findings were observed in fetuses from the high-dose group. Maternal toxicity was seen in the high-dose group but not at the lower doses where the findings were observed. Following oral administration of buprenorphine to rats, dose-related post-implantation losses, evidenced by increases in the numbers of early resorptions with consequent reductions in the numbers of fetuses, were observed at doses of 10 mg/kg/day or greater (21 times on a mg/m^2 basis). In the rabbit, increased post-implantation losses occurred at an oral dose of 40 mg/kg/day (169 times on a mg/m^2 basis). Following IM administration in the rat and the rabbit, post-implantation losses, as evidenced by decreases in live fetuses and increases in resorptions, occurred at 30 mg/kg/day (64 times and 127 times, respectively, on a mg/m^2 basis).

Buprenorphine was not teratogenic in rats and rabbits after subcutaneous (SC) doses of up to 5 mg/kg/day (9 and 5 times in rat, and 12 and 7 times in rabbit the highest daily exposure from 32 mg BRIXADI (weekly) or 128 mg BRIXADI (monthly), respectively, on an AUC basis), after intramuscular (IM) doses of up to 5 mg/kg/day (11 and 21 times on a mg/m^2 basis), after IV doses up to 0.8 mg/kg/day (2 and 3 times on a mg/m^2 basis), or after oral doses up to 160 mg/kg/day in rats (338 times on a mg/m^2 basis) and 25 mg/kg/day in rabbits (106 times on a mg/m^2 basis). Significant increases in skeletal abnormalities (e.g., extra thoracic vertebra or thoraco-lumbar ribs) were noted in rats after SC administration of 1 mg/kg/day and up (2.4 or 1.5 times the highest daily exposure from 32 mg BRIXADI (weekly) or 128 mg BRIXADI (monthly), respectively, on an AUC basis, but were not observed at oral doses up to 160 mg/kg/day (338 times on a mg/m^2 basis).

Increases in skeletal abnormalities in rabbits after IM administration of 5 mg/kg/day (21 times on a mg/m^2 basis) in the absence of maternal toxicity or oral administration of 1 mg/kg/day or greater (4 times on a mg/m^2 basis) were not statistically significant. In rabbits, buprenorphine produced statistically significant pre-implantation losses at oral doses of 1 mg/kg/day or greater (4 times on a mg/m^2 basis) and post-implantation losses that were statistically significant at IV doses of 0.2 mg/kg/day or greater (approximately equal on a mg/m^2 basis). No maternal toxicity was noted at doses causing post-implantation loss in this study.

Dystocia was noted in pregnant rats treated intramuscularly with buprenorphine from Gestation Day 14 through Lactation Day 21 at 5 mg/kg/day (11 times on a mg/m^2 basis). Fertility and pre- and post-natal development studies with buprenorphine in rats indicated increases in neonatal mortality after oral doses of 0.8 mg/kg/day and up (2 times on a mg/m^2 basis), after IM doses of 0.5 mg/kg/day and up (approximately equal on a mg/m^2 basis), and after SC doses of 0.1 mg/kg/day and up (0.4 or 0.3 times the highest daily exposure from 32 mg BRIXADI (weekly) or 128 mg BRIXADI (monthly), respectively, on an AUC basis). An apparent lack of milk production during these studies likely contributed to the decreased pup viability and lactation indices. Delays in the occurrence of righting reflex and startle response were noted in rat pups at an oral dose of 80 mg/kg/day (169 times on a mg/m^2 basis).

8.2 Lactation

Risk Summary

Based on two studies in 13 lactating women maintained on sublingual buprenorphine treatment, buprenorphine and its metabolite norbuprenorphine were present in low levels in human milk. Available data have not shown adverse reactions in breastfed infants. The development and health benefits of breastfeeding should be considered along with the mother's clinical need for buprenorphine treatment and any potential adverse effects on the breastfed child from the drug or from the underlying maternal condition.

Clinical Considerations

Advise the nursing mother taking buprenorphine to monitor the infant for increased drowsiness and breathing difficulties.

Data

Data were consistent from two studies (N=13) of breastfeeding infants whose mothers were maintained on sublingual doses of buprenorphine ranging from 2.4 to 24 mg/day, showing that the infants were exposed to less than 1% of the maternal daily dose.

In a study of six lactating women who were taking a median sublingual buprenorphine dose of 0.29 mg/kg/day 5 to 8 days after delivery, breast milk provided a median infant dose of 0.42 mcg/kg/day of buprenorphine and 0.33 mcg/kg/day of norbuprenorphine, equal to 0.2% and 0.12% respectively, of the maternal weight-adjusted dose (relative dose/kg [%] of norbuprenorphine was calculated from the assumption that buprenorphine and norbuprenorphine are equipotent).

Data from a study of seven lactating women who were taking a median (sublingual buprenorphine) dose of 7 mg/day an average of 1.12 months after delivery indicated that the mean milk concentrations (Cavg) of buprenorphine and norbuprenorphine were 3.65 mcg/L and 1.94 mcg/L respectively. Based on the study data, and assuming milk consumption of 150 mL/kg/day, an exclusively breastfed infant would receive an estimated mean absolute infant dose (AID) of 0.55 mcg/kg/day of buprenorphine and 0.29 mcg/kg/day of norbuprenorphine, or a mean relative infant dose (RID) of 0.38% and 0.18%, respectively, of the maternal weight-adjusted dose.

8.3 Females and Males of Reproductive Potential

Infertility

Chronic use of opioids may cause reduced fertility in females and males of reproductive potential. It is not known whether these effects on fertility are reversible [see Adverse Reactions (6.2), Clinical Pharmacology (12.2), Nonclinical Toxicology (13.1)].

8.4 Pediatric Use

The safety and effectiveness of BRIXADI have not been established in pediatric patients.

8.5 Geriatric Use

Clinical studies of BRIXADI did not include sufficient numbers of subjects aged 65 or older to determine whether they respond differently to the drug than younger patients. Other reported clinical experience with buprenorphine has not identified differences in responses between the geriatric and younger patients.

Due to possible decreased hepatic, renal, or cardiac function and of concomitant disease or other drug therapy in geriatric patients, the decision to prescribe BRIXADI should be made cautiously in individuals 65 years of age or older and these patients should be monitored for signs and symptoms of toxicity or overdose.

8.6 Hepatic Impairment

The effect of hepatic impairment on the pharmacokinetics of BRIXADI has not been studied.

The effect of hepatic impairment on the pharmacokinetics of sublingual buprenorphine has been evaluated in a pharmacokinetic study. While no clinically significant changes were observed in subjects with mild hepatic impairment, the plasma levels have been shown to be higher and half-life values have been shown to be longer for buprenorphine in subjects with moderate and severe hepatic impairment.

Because of the long-acting nature of the product, adjustments to dosages of BRIXADI are not rapidly reflected in plasma buprenorphine levels. Therefore, patients with pre-existing moderate to severe hepatic impairment are not candidates for treatment with BRIXADI.

Patients who develop moderate to severe hepatic impairment while being treated with BRIXADI should be monitored for signs and symptoms of toxicity or overdose caused by increased levels of buprenorphine [see Warnings and Precautions (5.14), Clinical Pharmacology (12.3)].

8.7 Renal Impairment

Clinical studies of BRIXADI did not include subjects with renal impairment. No differences in buprenorphine pharmacokinetics were observed between 9 dialysis-dependent and 6 normal patients following IV administration of 0.3 mg buprenorphine.

9 DRUG ABUSE AND DEPENDENCE

9.1 Controlled Substance

BRIXADI contains buprenorphine, a Schedule III substance under the Controlled Substances Act.

9.2 Abuse

Abuse is the intentional, non-therapeutic use of a drug, even once, for its desirable psychological or physiological effects. Misuse is the intentional use, for therapeutic purposes, of a drug by an individual in a way other than prescribed by a healthcare provider or for whom it was not prescribed.

BRIXADI contains buprenorphine, a Schedule III controlled substance that can be abused similar to other opioids. Patients who continue to misuse, abuse, or divert buprenorphine products or other opioids should be provided with or referred for more intensive and structured treatment. Abuse of buprenorphine poses a risk of overdose and death. This risk is increased with the abuse of buprenorphine and alcohol and other substances, especially benzodiazepines [see Warnings and Precautions (5.5)].

BRIXADI is distributed through a restricted distribution program, which is intended to prevent the direct distribution to a patient. BRIXADI should only be dispensed directly to a healthcare provider for administration by a healthcare provider. It is supplied in prefilled syringes and is intended for administration only by subcutaneous injection by a healthcare provider. The entire contents of the prefilled syringe should be administered. After administration, a small amount of BRIXADI may remain in the needle and syringe should be properly disposed of [see How Supplied/Storage and Handling (16)].

Upon injection, BRIXADI spontaneously transforms from a low viscous solution to a liquid crystalline gel that encapsulates buprenorphine and releases it at a steady rate as the depot biodegrades [see Warnings and Precautions (5.1)].

Clinical monitoring for evidence at the injection site of tampering or attempting to remove the depot should be ongoing throughout treatment. No attempts to remove BRIXADI have been reported in clinical trials.

9.3 Dependence

Physical dependence is a state that develops as a result of physiological adaptation in response to repeated drug use, manifested by withdrawal signs and symptoms after abrupt discontinuation or a significant dose reduction of a drug.

Buprenorphine is a partial agonist at the mu-opioid receptor and chronic administration produces physical dependence of the opioid type, characterized by moderate withdrawal signs and symptoms upon abrupt discontinuation or rapid taper. The withdrawal syndrome is typically milder than seen with full agonists and may be delayed in onset. Monitor patients during discontinuation of BRIXADI for symptoms of withdrawal [see Warnings and Precautions (5.8)].

Due to the long-acting nature of BRIXADI, withdrawal signs and symptoms may not be evident immediately following the discontinuation of treatment.

Neonatal opioid withdrawal syndrome (NOWS) is an expected and treatable outcome of prolonged use of opioids during pregnancy [see Warnings and Precautions (5.6)].

10 OVERDOSAGE

Clinical Presentation

The manifestations of acute buprenorphine overdose include pinpoint pupils, sedation, hypotension, hypoglycemia, respiratory depression, and death.

Toxic leukoencephalopathy has been reported after opioid overdose and can present hours, days, or weeks after apparent recovery from the initial intoxication.

Treatment of Overdose

In the event of overdose, the respiratory and cardiac status of the patient should be monitored carefully. When respiratory or cardiac functions are depressed, primary attention should be given to the re‐establishment of adequate respiratory exchange through provision of a patent airway and institution of assisted or controlled ventilation. Oxygen, IV fluids, vasopressors, and other supportive measures should be considered as indicated. An opioid overdose reversal agent may be of value for the management of buprenorphine overdose. Higher than normal doses and repeated administration may be necessary.

Clinicians should consider the potential role and contribution of buprenorphine, other opioids, and other CNS depressant drugs in a patient's clinical presentation.

11 DESCRIPTION

BRIXADI (buprenorphine) extended-release injection is a sterile, yellowish to yellow clear liquid provided in a single-dose, pre-filled syringe intended for subcutaneous injection only. BRIXADI is designed to deliver buprenorphine at a controlled rate over either one week or one month.

The active ingredient in BRIXADI is buprenorphine free base, a partial opioid agonist.

BRIXADI is provided in multiple doses with two durations (weekly and monthly).

- BRIXADI (weekly; 8, 16, 24, 32 mg) consists of 50 mg/mL buprenorphine. The inactive ingredients include dehydrated alcohol (12% v/v), glycerol dioleate (43% v/v), and soybean phosphatidylcholine (41% w/v).
- BRIXADI (monthly; 64, 96, 128 mg) consists of 356 mg/mL buprenorphine. The inactive ingredients include glycerol dioleate (24% v/v), methylpyrrolidone (31% v/v), and soybean phosphatidylcholine (15% w/v).

Upon injection, BRIXADI spontaneously transforms from a low viscous solution to a liquid crystalline gel that encapsulates buprenorphine and releases it at a steady rate as the depot biodegrades.

Different drug product strengths, or doses, are accomplished by different syringe fill volumes [see Dosage Forms and Strengths (3)].

The molecular weight of buprenorphine free base is 467.65 g/mol, and its molecular formula is C29H41NO4. Chemically, buprenorphine is: (2S)-2-[17-(Cyclopropylmethyl)-4,5α-epoxy-3-hydroxy-6α,14-ethano-14α-morphinan-7α-yl]-3,3-dimethylbutan-2-ol.

The structural formula is:

12 CLINICAL PHARMACOLOGY

12.1 Mechanism of Action

BRIXADI contains buprenorphine, a partial agonist at the mu-opioid receptor and an antagonist at the kappa-opioid receptor.

12.2 Pharmacodynamics

Opioid Blockade

The opioid blockade study assessed the blockade of subjective opioid drug-liking effects and pharmacokinetics (PK) of BRIXADI (weekly) in 47 patients with moderate or severe opioid dependence. The primary endpoint was the maximum rating (Emax) on the visual analogue scale (VAS) for drug-liking. After stabilization on immediate-release morphine, all patients completed a 3-day qualification/baseline hydromorphone challenge session consisting of 3 intramuscular doses of hydromorphone (0 mg, [placebo], 6 mg, and 18 mg) once daily for 3 consecutive days in a randomized, double-blind, crossover manner. Following the qualification phase, eligible patients received 2 injections of BRIXADI (weekly) for two weeks at either the 24 mg or 32 mg level. Two hydromorphone challenge sessions (3 consecutive days each) were conducted throughout the week after each weekly injection of BRIXADI (weekly).

On average, the subjective effects (e.g., drug liking [Emax]) of 6 mg or 18 mg hydromorphone was blocked following injections of BRIXADI (weekly) at the 24 mg or 32 mg levels. The variability in drug-liking scores was wider for the 18 mg than the 6 mg hydromorphone dose level. In addition, for the 18 mg hydromorphone dose challenge, the drug-liking score variability was wider towards the end of the BRIXADI (weekly) dosing interval compared to earlier in the interval (e.g. Days 4-6 versus Days 1-3; Day 11-13 versus Day 8-10). Drug-liking score variability was wider for the 24 mg BRIXADI (weekly) dose level compared to 32 mg [see Clinical Studies (14.1)].

Figure 14 illustrates the relationship between buprenorphine plasma level and drug liking after 18 mg hydromorphone where data from the 24 mg BRIXADI (weekly) arm is pooled with data from the 32 mg BRIXADI (weekly) arm. The observed plateau for maximal response of drug-liking was reached at buprenorphine concentrations of approximately 1.5-2 ng/mL plasma levels.

Figure 14: Placebo-Corrected Drug Liking VAS vs. Plasma Buprenorphine Concentration Following 18 mg Hydromorphone Challenges for Pooled 24 mg and 32 mg Arms

Androgen Deficiency

Chronic use of opioids may influence the hypothalamic-pituitary-gonadal axis, leading to androgen deficiency that may manifest as low libido, impotence, erectile dysfunction, amenorrhea, or infertility.

The causal role of opioids in the clinical syndrome of hypogonadism is unknown because the various medical, physical, lifestyle, and psychological stressors that may influence gonadal hormone levels have not been adequately controlled for in studies conducted to date. Patients presenting with symptoms of androgen deficiency should undergo laboratory evaluation.

Cardiac Electrophysiology

Thorough QT studies with buprenorphine products have demonstrated modest QT prolongation ≤15 msec. Two categorical analyses of cardiovascular-specific adverse events among patients exposed to buprenorphine demonstrated no proarrhythmic potential. One Holter monitoring study demonstrated no arrhythmia. An analysis of medical literature provided no evidence for causal association between buprenorphine and Torsades de Pointes.

Physiological Effects

Buprenorphine in IV (2, 4, 8, 12 and 16 mg) and sublingual (12 mg) doses have been administered to opioid-experienced subjects who were not physically dependent to examine cardiovascular, respiratory, and subjective effects at doses comparable to those used for treatment of opioid use disorder. Compared to placebo, there were no statistically significant differences among any of the treatment conditions for blood pressure, heart rate, respiratory rate, O2 saturation, or skin temperature across time. Systolic BP was higher in the 8 mg group than placebo (3-hour AUC values). Minimum and maximum effects were similar across all treatments. Subjects remained responsive to low voice and responded to computer prompts. Some subjects showed irritability, but no other changes were observed.

The respiratory effects of sublingual buprenorphine were compared with the effects of methadone in a double-blind, parallel group, dose ranging comparison of single doses of buprenorphine sublingual solution (1, 2, 4, 8, 16, or 32 mg) and oral methadone (15, 30, 45, or 60 mg) in non-dependent, opioid-experienced volunteers. In this study, hypoventilation not requiring medical intervention was reported more frequently after buprenorphine doses of 4 mg and higher than after methadone. Both drugs decreased O2 saturation to the same degree.

In clinical studies conducted with BRIXADI at doses ranging from 7.5 to 32 mg for weekly BRIXADI and 64 to 192 mg for monthly BRIXADI, no incidences of temperature elevations, or clinically significant lowering of oxygen saturation were observed.

12.3 Pharmacokinetics

Absorption

BRIXADI is an extended-release formulation of buprenorphine designed for subcutaneous administration. BRIXADI is available in two regimens: weekly and monthly. Following single doses of BRIXADI (weekly) or BRIXADI (monthly), the buprenorphine Cmax and AUCinf increase dose-proportionally.

The steady-state PK of buprenorphine following BRIXADI (weekly), BRIXADI (monthly) and their comparison to sublingual SUBUTEX across three studies are shown in Table 8. In these studies, BRIXADI (weekly) was administered for 4 or 4 to 7 weekly doses, BRIXADI (monthly) was administered for 4 monthly doses, and SUBUTEX was administered for 7 daily doses.

After BRIXADI subcutaneous injection, the buprenorphine plasma concentration increases with a median time to maximum plasma concentration (tmax) of about 24 hours for BRIXADI (weekly) and 6-10 hours for BRIXADI (monthly). Based on trough levels after each dose, steady-state exposure is reached at administration of the fourth weekly or monthly dose.

After four repeated doses of BRIXADI (weekly) (16 mg) AUCτ (0-7d), Cmax and Ctrough values are ~40% higher exposure compared to the first dose. Based on cross-study comparisons, four repeated doses of BRIXADI (monthly) (128 mg) results in 68%, 65%, and 124% higher AUCτ (0-28d), Cmax and Ctrough values, respectively compared to the first dose.

Table 8: Summary of steady-state PK parameters of buprenorphine after subcutaneous buttock injections of BRIXADI (weekly) and BRIXADI (monthly) and sublingual (SL) administration of SUBUTEX
Drug product dose |  |  | Cav (ng/mL) |  |  | Cmax (ng/mL) |  |  | Ctrough [C168h after 4th dose for BRIXADI (weekly), C28d after 4th dose for BRIXADI (monthly) and C24h after 7th daily dose for Subutex] (ng/mL)
SL BPN | Brixadi (weekly) | Brixadi (monthly) | SL BPN [Average value of two studies] | Brixadi (weekly) | Brixadi (monthly) | SL BPN | Brixadi (weekly) | Brixadi (monthly) | SL BPN | Brixadi (weekly) | Brixadi (monthly)
8 mg | 16 mg | 64 mg | 1.2 | 2.1 | 2.0 [Simulated] | 4.7 | 4.3 | 4.0 | 0.7 | 0.8 | 1.3
16 mg | 24 mg | 96 mg | 1.8 | 2.9 | 2.9 | 6.5 | 5.5 | 6.0 | 1.0 | 1.4 | 2.0
24 mg | 32 mg | 128 mg | 2.5 | 4.2 | 3.9 | 8.2 | 6.9 | 11.1 | 1.4 | 2.6 | 2.1

Effect of injection Site on PK of BRIXADI

After multiple dose subcutaneous injections of 32 mg BRIXADI weekly product at different injection sites (abdomen, thigh, buttock or upper arm), a comparable PK exposure was observed. However, injection in the arm site was associated with approximately 10% lower plasma levels than other sites.

Distribution:

Buprenorphine is approximately 96% protein bound, primarily to alpha and beta globulin.

Elimination:

Buprenorphine is metabolized and eliminated in urine and feces. The apparent terminal plasma half-life of buprenorphine following subcutaneous injection of BRIXADI ranged between 3 to 5 days for BRIXADI (weekly) and 19 to 26 days for BRIXADI (monthly) as a result of the slow release of buprenorphine from the subcutaneous depot.

Metabolism:

Buprenorphine undergoes both N-dealkylation to norbuprenorphine and glucuronidation. The N-dealkylation pathway is mediated primarily by the CYP3A4. Norbuprenorphine, the major metabolite, can further undergo glucuronidation. Norbuprenorphine has been found to bind opioid receptors in vitro; however, it has not been studied clinically for opioid-like activity.

Norbuprenorphine steady-state plasma concentrations in humans after subcutaneous injection of BRIXADI (weekly or monthly) are low compared to buprenorphine (AUC norbuprenorphine/ buprenorphine ratio of 0.35).

Excretion:

A mass balance study of buprenorphine showed complete recovery of radiolabel in urine (30%) and feces (69%) collected up to 11 days after dosing. Almost all of the dose was accounted for in terms of buprenorphine, norbuprenorphine, and two unidentified buprenorphine metabolites. In urine, most of the buprenorphine and norbuprenorphine was conjugated (buprenorphine, 1% free and 9.4% conjugated; norbuprenorphine, 2.7% free and 11% conjugated). In feces, almost all of the buprenorphine and norbuprenorphine were free (buprenorphine, 33% free and 5% conjugated; norbuprenorphine, 21% free and 2% conjugated).

Drug Interaction Studies:

CYP3A4 Inhibitors and Inducers

The effects of co-administered CYP3A4 inhibitors and inducers on buprenorphine exposure in subjects treated with BRIXADI have not been studied; however, such interactions have been established in studies using transmucosal buprenorphine. The effects of buprenorphine may be dependent on the route of administration.

Buprenorphine is metabolized to norbuprenorphine primarily by cytochrome CYP3A4; therefore, potential interactions may occur when BRIXADI is given concurrently with agents that affect CYP3A4 activity. The effects of co-administered CYP3A4 inducers or inhibitors have been established in studies using transmucosal buprenorphine. Patients who switch to BRIXADI treatment from a regimen for transmucosal buprenorphine used concomitantly with CYP3A4 inhibitors (e.g., ketoconazole, macrolide antibiotics (e.g., erythromycin) or HIV protease inhibitors, or CYP3A4 inducer (e.g., phenobarbital, carbamazepine, phenytoin, rifampicin) should be monitored to ensure that the plasma buprenorphine level provided by BRIXADI is adequate and not excessive [see Drug Interactions (7)].

Buprenorphine has been found to be a CYP2D6 and CYP3A4 inhibitor and its major metabolite, norbuprenorphine, has been found to be a moderate CYP2D6 inhibitor in in vitro studies employing human liver microsomes. However, plasma concentrations of buprenorphine and norbuprenorphine resulting from therapeutic BRIXADI doses are not expected to significantly affect the metabolism (systemic exposure) of other concomitantly administered medications [see Drug Interactions (7)].

Specific Populations

Based on population pharmacokinetic analyses, age, sex and race do not have a clinically meaningful effect on PK of BRIXADI.

Hepatic Impairment

The effect of hepatic impairment on the pharmacokinetics of BRIXADI has not been studied.

In a pharmacokinetic study, the disposition of buprenorphine was determined after administering a 2.0/0.5 mg Suboxone (buprenorphine/naloxone) sublingual tablet in subjects with varied degrees of hepatic impairment as indicated by Child-Pugh criteria. The disposition of buprenorphine in patients with hepatic impairment was compared to disposition in subjects with normal hepatic function.

In subjects with mild hepatic impairment, the changes in mean Cmax, AUC0-last, and half-life values of buprenorphine were not clinically significant.

For subjects with moderate and severe hepatic impairment, mean Cmax, AUC0-last, and half-life values of buprenorphine were increased [see Warnings and Precautions (5.14) and Use in Specific Populations (8.6)].

Renal Impairment

The effect of renal impairment on the pharmacokinetics of BRIXADI has not been studied. Clinical studies of BRIXADI did not include subjects with severe renal impairment. Less than 1% is excreted as unchanged buprenorphine in urine following IV buprenorphine administration. No differences in buprenorphine pharmacokinetics were observed between 9 dialysis-dependent and 6 normal patients following IV administration of 0.3 mg buprenorphine [see Use in Specific Populations (8.7)].

Population PK analyses indicated no notable relationship between creatinine clearance and steady-state buprenorphine plasma concentrations.

HCV infection

In subjects with HCV infection but no sign of hepatic impairment, the changes in the mean Cmax, AUC0-last, and half-life values of buprenorphine were not clinically significant in comparison to healthy subjects without HCV infection.

13 NONCLINICAL TOXICOLOGY

13.1 Carcinogenesis, Mutagenesis, Impairment of Fertility

Carcinogenicity

Carcinogenicity studies of buprenorphine were conducted in Sprague-Dawley rats and CD-1 mice. Buprenorphine was administered in the diet to rats for 27 months at doses of 0.6, 5.5, and 56 mg/kg/day (0.3, 1.4 and 11.3 times the highest daily exposure from 32 mg BRIXADI (weekly) on an AUC basis and 0.2, 0.9 and 6.9 times the highest daily exposure from 128 mg BRIXADI (monthly) on an AUC basis). A statistically significant dose-related increase in Leydig cell tumors occurred. In an 86-week study in CD-1 mice, buprenorphine was not carcinogenic at dietary doses up to 100 mg/kg/day (7 and 4 times the highest daily exposure from 32 mg BRIXADI (weekly) or 128 mg BRIXADI (monthly), respectively, on an AUC basis).

NMP, an excipient in BRIXADI (monthly) produced an increase in hepatocellular adenomas and carcinomas in male and female mice at 47 and 60 times, respectively, the maximum daily dose (MDD) of NMP via 128 mg BRIXADI (monthly) on a mg/m^2 basis. The clinical significance of these findings is unclear. No tumors were noted in male or female mice at 7.4 and 9.5 times the MDD on a mg/m^2 basis. In 2-year inhalation and dietary studies in rats, NMP did not result in evidence of carcinogenicity.

Mutagenicity

Buprenorphine was studied in a series of tests utilizing gene, chromosome, and DNA interactions in both prokaryotic and eukaryotic systems. Results were negative in yeast (S. cerevisiae) for recombinant, gene convertant, or forward mutations; negative in Bacillus subtilis "rec" assay; negative for clastogenicity in CHO cells, Chinese hamster bone marrow and spermatogonia cells, and negative in the mouse lymphoma L5178Y assay.

Results were equivocal in the Ames test: negative in studies in two laboratories, but positive for frame shift mutation at a high dose (5 mg/plate) in a third study. Results were positive in the Green-Tweets (E. coli) survival test, positive in a DNA synthesis inhibition (DSI) test with testicular tissue from mice, for both in vivo and in vitro incorporation of [^3 H]thymidine, and positive in unscheduled DNA synthesis test using testicular cells from mice.

Impairment of Fertility

Reproduction studies of buprenorphine in rats demonstrated no evidence of impaired fertility at daily oral doses up to 80 mg/kg/day (169 times the mean daily dose of 4.6 mg buprenorphine as delivered by 32 mg BRIXADI (weekly) or 128 mg BRIXADI (monthly) on a mg/m^2 basis) or up to 5 mg/kg/day IM (11 times the mean daily dose of 4.6 mg buprenorphine as delivered by 32 mg BRIXADI (weekly) or 128 mg BRIXADI (monthly) on a mg/m^2 basis) or 5 mg/kg/day SC (16 or 10 times the highest daily exposure from 32 mg BRIXADI (weekly) or 128 mg BRIXADI (monthly), respectively, on an AUC basis).

14 CLINICAL STUDIES

The key studies from the BRIXADI clinical development program that support its use in the treatment of moderate to severe opioid use disorder are a Phase 3, double-blind, active control (sublingual buprenorphine/naloxone), efficacy and safety study (NCT02651584), and an opioid blockade study (NCT02611752). Additionally, a Phase 3, open-label safety study (NCT0267211) provides data to support the safety of converting from daily transmucosal buprenorphine, buprenorphine/naloxone or generic equivalents.

14.1 Opioid Blockade Study, NCT02611752

The opioid blockade study assessed the blockade of subjective opioid effects, PK, and safety of BRIXADI weekly in 47 patients with moderate or severe opioid use disorder. Forty-six patients completed the study. Subjects were randomized to receive two injections of BRIXADI (weekly) once weekly for 2 weeks either at a 24 mg or 32 mg dose level.

After stabilization on immediate-release morphine, all patients completed a 3-day qualification/baseline hydromorphone (HM) challenge session, which included intramuscular administration of 3 doses of HM (0 mg [placebo], 6 mg and 18 mg) once daily for 3 consecutive days. Patients were not exposed to buprenorphine during the baseline/qualification phase.

Following the qualification phase, eligible patients were randomly assigned to receive 2 doses of either 24 mg (22 patients) or 32 mg (24 patients) BRIXADI (weekly) with each dose administered one week apart. Two HM challenge sessions (Days 1-3 and 4-6 for the first session and Days 8-10 and 11-13 for the second session, respectively) were conducted after each dose of BRIXADI (weekly).

The primary endpoint was the peak effect (Emax) on a 100-mm bipolar (i.e., 50=neutral response) "Drug Liking" Visual Analog Scale (VAS). The pre-defined upper bound of the 95% CI for complete blockade of drug liking was an 11 mm difference between VAS Emax scores obtained for HM doses compared with placebo.

During the qualification/baseline phase, mean Emax scores for placebo were neutral while intramuscular hydromorphone 6 and 18 mg produced dose-related increases in the scores. Beginning with the first injection of BRIXADI (weekly) 24 mg or 32 mg weekly, no active intramuscular hydromorphone dose resulted in a mean drug liking VAS Emax score of 11 mm or greater when compared to placebo, which demonstrated complete blockade that was sustained throughout the first and second dosing intervals (see Figure 15). Individual subject scores are shown in Figure 16.

Figure 15: Mean Difference in Placebo-Corrected Peak Drug Liking

Figure 16: Mean Difference in Placebo-Corrected Peak Drug Liking with Individual Scores

14.2 Phase 3 Double-Blind Study, NCT02651584

The efficacy and safety of BRIXADI for the treatment of opioid use disorder was evaluated in a Phase 3, 24-Week, randomized, double-blind, double-dummy, active controlled, multicenter study in patients who met the DSM-5 criteria for moderate or severe opioid use disorder and who were actively seeking but not currently receiving buprenorphine treatment. Patients were randomized to receive either BRIXADI injections with placebo sublingual tablets or sublingual buprenorphine/naloxone (SL BPN/NX) tablets with placebo injections. All patients received individual drug counseling for the duration of the study.

On the first day of treatment patients received an open-label 4 mg test dose of sublingual buprenorphine. Patients who tolerated the test dose (two patients did not tolerate the test dose) were randomized and given a 16 mg injection of BRIXADI (weekly) or matched placebo. During the next 6 days patients were allowed up to two further 8 mg injections as needed. Patients received an injection of 16, 24, or 32 mg on Day 8 matched to the dose they received in the previous seven days. Patients received injections weekly (every 7 days +/- 2-day window) for twelve weeks total and then transitioned to an equivalent dose of BRIXADI (monthly) (every 28 days, +/- 7-day window) for the remaining twelve weeks. Dose adjustments were permitted for the duration of the study. Supplemental 8 mg BRIXADI (weekly) injections were allowed during the second phase of the study and were also used in the active-controlled group. Overall, supplemental 8 mg injections were given to 14 patients (6.6%) in the BRIXADI arm and 17 patients (7.9%) in the SL BPN/NX arm. Table 8 shows the doses of BRIXADI (weekly) administered following the initial titration period and at the final visit before transition to BRIXADI (monthly) was allowed. Table 9 shows the first and final BRIXADI (monthly) dose administered to each patient.

Table 9: Number of patients receiving each BRIXADI (weekly) dose at selected time points
BRIXADI (weekly) Dose | Following Titration Period | End of Weekly Phase
16 mg | 2 | 6
24 mg | 128 | 84
32 mg | 54 | 64

Table 10: Number of patients receiving each BRIXADI (monthly) dose at selected time points
BRIXADI (monthly) Dose | First BRIXADI (monthly) dose | Final BRIXADI (monthly) dose
64 mg | 8 | 11
96 mg | 84 | 83
128 mg | 66 | 56
160 mg [not an approved strength] | 0 | 8

For the first twelve weeks patients completed weekly visits. For the final twelve weeks patients were transitioned to monthly visits. Patients were also required to complete three additional randomly scheduled visits during the final twelve weeks. Efficacy was evaluated using urine drug screens combined with self-reported use of illicit opioid use. Missing urine drug screen samples and/or self-reports were counted as positive for illicit opioids.

A total of 428 patients were randomized equally (215 patients in the SL BPN/NX group and 213 in the BRIXADI group). Of the randomized patients, 69.0% (147/213) of the patients in BRIXADI treatment group and 72.6% (156/215) of the patients in the SL BPN/NX treatment group completed the 24-week period. Patient demographics and baseline characteristics are provided in Table 11.

Table 11: Patient Demographics and Baseline Characteristics
 | BRIXADI (N=213) | SL BPN/NX (N=215)
Mean Age (Years) | 38.7 | 38.0
Sex %
Male | 56.8 | 66.0
Female | 43.2 | 34.0
Race or Ethnicity %
White | 74.6 | 76.3
Black or African American | 22.1 | 22.3
American Indian or Alaska Native | 0.9 | 0.5
Asian | 0.5 | 0
Native Hawaiian or Other Pacific Islander | 0.5 | 0
Other | 1.4 | 0.9
Primary Opioid of Use at Initiation %
Heroin | 71.4 | 70.2
Prescription Pain Reliever | 28.6 | 29.8
Injectable Route % | 53.5 | 51.2
Substance Use by Urine Toxicology Prior to Randomization %
Amphetamines | 22.1 | 18.6
Barbiturates | 1.4 | 0.5
Benzodiazepine | 21.1 | 21.9
Cocaine | 30.5 | 32.6
Cannabinoids | 34.3 | 36.3
Fentanyl | 29.1 | 22.8
Phencyclidine | 1.9 | 0.5
Medical History %
Anxiety | 14.1 | 18.6
Back Pain | 15.5 | 18.6
Depression | 11.7 | 13.0

Table 12 below illustrates the proportion of patients who were considered to be responders. A patient was a responder if they met all of the following criteria:

- Negative opioid assessment (urinalysis and self-report) during week 12 (evaluated during week 13 visit).
- No more than one positive opioid assessment in the three illicit opioid use assessments performed during week 9 to 11 (evaluated during visits at weeks 10 to 12).
- Negative opioid assessment during the final month of the study.
- No more than one positive opioid assessment at the three scheduled monthly visits and three random site visits.

This responder definition was designed to identify patients who were successfully treated with both BRIXADI (weekly) (administered in the first 12 weeks of treatment) and BRIXADI (monthly) (administered in the second 12 weeks of treatment). Therefore, patients were required to have negative opioid assessments at the end of each treatment phase. Each phase also included an allowable grace period (an initial period of time when positive opioid assessments were not taken into account) and the definition also allowed for sporadic positive assessments. Based on the results of this trial, the efficacy of BRIXADI was demonstrated. Table 12 shows the response rate for each treatment arm along with the associated 95% confidence interval for their difference.

Table 12: Number (Percentage) of Patients who met the Responder Definition
BRIXADI Injection with placebo sublingual tablets (N=213) | SL BPN/NX Tablets with Placebo Injections (N=215) | Treatment Difference (95% CI)
36 (16.9%) | 30 (14.0%) | 2.9% (-3.9%, 9.8%) [The lower bound of the confidence interval was within the agreed upon noninferiority threshold of −10%.]

The cumulative distribution function (CDF) of the percentage of negative opioid assessments (urine samples negative for illicit opioid use combined with self-reports negative for illicit opioid use) from Week 4 through Week 24 are shown in Figure 17 and Table 13. The figure and table are cumulative, so that a patient whose percentage of opioid-free assessments is, for example 50%, is also included at every level of negative opioid assessments below 50%. Missing values and values after premature discontinuation were considered positive. Based on the CDF of the percentage of negative opioid assessments, superiority was demonstrated with BRIXADI with statistical significance compared with SL BPN/NX. However, on the right-hand side of the curves where patients were reporting mostly negative opioid assessments (80% or greater) there was little to no difference between BRIXADI and SL BPN/NX.

Figure 17: Patients Achieving Varying Percentages of Negative Opioid Assessments (urine and self-report) in weeks 4 through 24

Table 13: Patients Achieving Varying Percentage of Opioid-Negative Assessments (urine and self report) (Weeks 4-24)
Percentage of Opioid-Negative Assessments (Urine and Self Report) | Number (%) of Patients
Percentage of Opioid-Negative Assessments (Urine and Self Report) | BRIXADI N=213 | SL BPN/NX N=215
≥ 0% | 213 (100.0) | 215 (100.0)
≥ 10% | 121 (56.8) | 87 (40.5)
≥ 20% | 114 (53.5) | 79 (36.7)
≥ 30% | 95 (44.6) | 67 (31.2)
≥ 40% | 85 (39.9) | 62 (28.8)
≥ 50% | 74 (34.7) | 56 (26.0)
≥ 60% | 68 (31.9) | 53 (24.7)
≥ 70% | 51 (23.9) | 49 (22.8)
≥ 80% | 44 (20.7) | 43 (20.0)
≥ 90% | 28 (13.1) | 27 (12.6)
≥ 100% | 23 (10.8) | 14 (6.5)

16 HOW SUPPLIED/STORAGE AND HANDLING

Weekly and monthly BRIXADI is available as a sterile, yellowish to yellow clear liquid solution in a single dose, prefilled safety syringe.

The BRIXADI needle cap is synthetically derived from natural rubber latex, which may cause allergic reactions in latex sensitive individuals.

STORAGE AND HANDLING

Store BRIXADI at room temperature at 20°C to 25°C (68°F to 77° F); with excursions permitted at 15°C to 30° C (59°F to 86°F) [see USP Controlled Room Temperature].

BRIXADI is a Schedule III drug product. Handle with adequate security and accountability. After administration, syringes should be properly disposed, per facility procedure for a Schedule III drug product, and per applicable federal, state, and local regulations.

BRIXADI Weekly
50 mg/mL buprenorphine
Dosage | Volume | NDC
8 mg | 0.16 mL | 58284-208-01 58284-208-91
16 mg | 0.32 mL | 58284-216-01 58284-216-91
24 mg | 0.48 mL | 58284-224-01 58284-224-91
32 mg | 0.64 mL | 58284-232-01 58284-232-91

BRIXADI Monthly
356 mg/mL buprenorphine
Dosage | Volume | NDC
64 mg | 0.18 mL | 58284-264-01 58284-264-91
96 mg | 0.27 mL | 58284-296-01 58284-296-91
128 mg | 0.36 mL | 58284-228-01 58284-228-91

17 PATIENT COUNSELING INFORMATION

Advise the patient to read the FDA-approved patient labeling (Medication Guide).

Instruct patients to read the Medication Guide each time BRIXADI is administered because new information may be available.

Safe Use

Before initiating treatment with BRIXADI, explain the points listed below to patients and caregivers.

BRIXADI Risk Evaluation and Mitigation Strategy (REMS)

Advise patients that because of the risk of serious harm or death due to intravenous self-administration, BRIXADI is available only through a restricted distribution program called the BRIXADI REMS. Healthcare settings and pharmacies are certified and only dispense BRIXADI directly to a healthcare provider for administration by a healthcare provider [see Warnings and Precautions (5.2)].

Life Threatening Respiratory Depression

Educate patients and caregivers on how to recognize respiratory depression and emphasize the importance of calling 911 or getting emergency medical help right away in the event of a known or suspected overdose [see Warnings and Precautions 5.4)].

Patient Access to an Opioid Overdose Reversal Agent for the Emergency Treatment of Opioid Overdose

Inform patients and caregivers about opioid overdose reversal agents (e.g., naloxone, nalmefene) and discuss the importance of having access to an opioid overdose reversal agent. Because patients being treated for opioid use disorder are at risk for relapse, discuss the importance of having access to an opioid overdose reversal agent. Also discuss the importance of having access to an opioid overdose reversal agent if there are householdmembers (including children) or other close contacts at risk for accidental ingestion or opioid overdose.

Discuss with the patient the options for obtaining an opioid overdose reversal agent (e.g., prescription, over-the-counter (some products), or as part of a community-based program) [see Dosage and Administration (2.2), Warnings and Precautions (5.4)].

There are important differences among the opioid overdose reversal agents, such as route of administration, product strength, approved patient age range, and pharmacokinetics. Be familiar with these differences, as outlined in the approved labeling for those products, prior to recommending or prescribing such an agent.

Educate patients and caregivers on how to recognize the signs and symptoms of an opioid overdose.

Explain to patients and caregivers that effects of opioid overdose reversal agents like naloxone and nalmefene are temporary, and that they must call 911 or get emergency medical help right away in all cases of known or suspected opioid overdose, even if an opioid overdose reversal agent is administered.

Repeat administration may be necessary, particularly for overdose involving buprenorphine. [see Dosage and Administration (2.2), Warnings and Precautions (5.4), Overdosage (10)].

Advise patients and caregivers:

- how to treat with an opioid overdose reversal agent in the event of an opioid overdose
- to tell family and friends about their opioid overdose reversal agent and to keep it in a place where family and friends can easily access it in an emergency
- to read the Patient Information (or other educational material) that will come with their opioid overdose reversal agent. Emphasize the importance of doing this before an opioid emergency happens, so the patient and caregiver will know what to do.

Interaction with Benzodiazepines and other CNS Depressants

Inform patients and caregivers that potentially fatal additive effects may occur if BRIXADI is used with benzodiazepines or other CNS depressants, including alcohol, and not to use these concomitantly unless supervised by a healthcare provider [see Warnings and Precautions (5.5) and Drug Interactions (7)].

Serotonin Syndrome

Inform patients that BRIXADI could cause a rare but potentially life-threatening condition resulting from concomitant administration of serotonergic drugs. Warn patients of the symptoms of serotonin syndrome and to seek medical attention right away if symptoms develop. Instruct patients to inform their physicians if they are taking, or plan to take serotonergic medications [see Drug Interactions (7)].

Adrenal Insufficiency

Inform patients that BRIXADI could cause adrenal insufficiency, a potentially life-threatening condition. Adrenal insufficiency may present with non-specific symptoms and signs such as nausea, vomiting, anorexia, fatigue, weakness, dizziness, and low blood pressure. Advise patients to seek medical attention if they experience a constellation of these symptoms [see Warnings and Precautions (5.7)].

Anaphylaxis

Inform patients that anaphylaxis has been reported with buprenorphine. Advise patients how to recognize such a reaction and when to seek medical attention [see Warnings and Precautions (5.10)].

Latex Allergy

The BRIXADI needle cap is synthetically derived from natural rubber latex which may cause allergic reactions in latex-sensitive individuals [see Warnings and Precautions (5.10)].

Dependence and Withdrawal

Inform patients that BRIXADI can cause drug dependence and that withdrawal signs and symptoms may occur when the medication is discontinued [see Warnings and Precautions (5.11)].

Driving or Operating Heavy Machinery

Caution patients that BRIXADI may impair the mental or physical abilities required for the performance of potentially dangerous tasks such as driving or operating hazardous machinery.

Instruct patients not to drive or operate hazardous machinery until they are reasonably certain that BRIXADI therapy does not adversely affect their ability to engage in such activities [see Warnings and Precautions (5.16)].

Orthostatic Hypotension

Inform patients that, like other opioids, BRIXADI may produce orthostatic hypotension in ambulatory individuals [see Warnings and Precautions (5.17)].

Long Duration of Action

Inform patients that they may have detectable levels of buprenorphine for a prolonged period of time after treatment with BRIXADI. Considerations of drug-drug interactions, buprenorphine effects, and analgesia may continue to be relevant for several months after the last injection [see Clinical Pharmacology (12.3)].

Drug Interactions

Instruct patients to inform their healthcare providers of any other prescription medications, over-the-counter medications, or herbal preparations that are prescribed or currently being used [see Drug Interactions (7)].

Pregnancy

Neonatal Opioid Withdrawal Syndrome

Advise women that if they are pregnant while being treated with BRIXADI, the baby may have signs of withdrawal at birth and that withdrawal is treatable [see Warnings and Precautions (5.6), Use in Specific Populations (8.1)].

Embryofetal Toxicity

Advise women of childbearing potential who become pregnant or are planning to become pregnant to consult their healthcare provider regarding the possible effects of using BRIXADI during pregnancy [see Use in Specific Populations (8.1)].

Lactation

Warn patients that buprenorphine passes into breast milk. Advise the nursing mother taking buprenorphine to monitor the infant for increased drowsiness and breathing difficulties [see Use in Specific Populations (8.2)].

Infertility

Inform patients that chronic use of opioids may cause reduced fertility. It is not known whether these effects on fertility are reversible [see Infertility (8.3)].

Emergency Analgesia

Advise patients to instruct their family members to, in the event of emergency, inform the treating physician or emergency room staff that the patient is physically dependent on an opioid and that the patient is being treated with BRIXADI [see Warnings and Precautions (5.12)].

Clinical Monitoring

Tell your patients to seek emergency attention if they have signs or symptoms of respiratory or CNS depression or overdose [see Warnings and Precautions (5.4, 5.5)].

Tell your patients not to tamper with or try to remove their depot [see Dosage and Administration (2.5)].

© 2025 Braeburn, Inc. BRIXADI® is a registered trademark of Braeburn Inc.

Distributed by:
Braeburn Inc.
Plymouth Meeting, PA 19462

Manufactured by:
Pharmaceutics International, Inc. (Pii)
Cockeysville, MD 21030

BRX-PI-003

Medication Guide
BRIXADI® (brix-a-dee) (buprenorphine) extended-release injection, for subcutaneous use (CIII)

What is the most important information I should know about BRIXADI?

- Because of the serious risk of potential harm or death from self-injecting BRIXADI into a vein (intravenously), it is only available through a restricted program called the BRIXADI REMS Program.
  - BRIXADI is not available in retail pharmacies.
  - Your BRIXADI injection will only be given to you by a healthcare provider.
- BRIXADI contains a medicine called buprenorphine. Buprenorphine is an opioid that can cause serious and life-threatening breathing problems, especially if you take or use certain other medicines or drugs.
- Ask your healthcare provider about medicines like naloxone or nalmefene that can be used in an emergency to reverse opioid overdose. If a medication is given to reverse opioid overdose, you must call 911 or get emergency medical help right away to treat an overdose or accidental use of an opioid.
- BRIXADI can cause serious and life-threatening breathing problems. Get emergency help right away if you:
  - feel faint
  - feel dizzy
  - are confused
  - feel sleepy or uncoordinated
  - have blurred vision
  - have slurred speech
  - are breathing slower than normal
  - cannot think well or clearly
- Do not take BRIXADI with certain medicines. Taking BRIXADI with other opioid medicines, benzodiazepines, gabapentinoids (gabapentin or pregabalin), alcohol, other central nervous system depressants (including street drugs) can cause severe drowsiness, decreased awareness, breathing problems, coma, and death.
- In an emergency, have family members tell the emergency department staff that you are physically dependent on an opioid and are being treated with BRIXADI.
- You may have detectable levels of BRIXADI in your body for several months after stopping treatment with BRIXADI.

What is BRIXADI?
BRIXADI is a prescription medicine used to treat moderate to severe opioid addiction (dependence) to opioid drugs (prescription or illegal) in people:

- who have started treatment with a single dose of a buprenorphine medicine in the form of a sublingual tablet or buccal film (transmucosal), OR
- who are already being treated with buprenorphine

BRIXADI should be used as part of a complete treatment plan that also includes counseling and behavioral therapy. It is not known if BRIXADI is safe and effective in children.

Who should not receive BRIXADI?
Do not receive BRIXADI if you are allergic to buprenorphine or any ingredients in BRIXADI. See the end of this Medication Guide for a list of ingredients in BRIXADI .

Before receiving BRIXADI, tell your healthcare provider about all of your medical conditions, including if you have:

- trouble breathing or lung problems
- a curve in your spine that affects your breathing
- Addison's disease
- an enlarged prostate (men)
- problems urinating
- liver, kidney, or gallbladder problems
- a history of alcoholism
- a head injury or brain problem
- mental health problems
- adrenal gland or thyroid gland problems
- a latex allergy. The BRIXADI needle cap contains latex.

Tell your healthcare provider if you are:

- pregnant or plan to become pregnant. If you receive BRIXADI while pregnant, your baby may have symptoms of opioid withdrawal at birth that could be life-threatening if not recognized and treated. Talk to your healthcare provider if you are pregnant or become pregnant.
- breastfeeding. BRIXADI can pass into your breast milk and may harm your baby. Talk to your healthcare provider about the best way to feed your baby during treatment with BRIXADI. Monitor your baby for increased drowsiness and breathing problems if you breastfeed during treatment with BRIXADI.

Tell your healthcare provider about all the medicines you take, including prescription and over-the-counter medicines, vitamins and herbal supplements. Talk with your healthcare provider before starting any new medicines during or after stopping treatment with BRIXADI.

How will I receive BRIXADI?

- You will receive BRIXADI by your healthcare provider as an injection just under the skin (subcutaneous) of your buttock, thigh, stomach (abdomen), or upper arm. If you are new to buprenorphine treatment, the upper arm should only be used after 4 doses of BRIXADI.
- If you are not currently receiving buprenorphine treatment, your healthcare provider will give you a test dose of buprenorphine first to see if you are able to tolerate it, and then switch you over to BRIXADI.
- You will receive BRIXADI 1 time every week or 1 time every month.
- BRIXADI is injected as a liquid. After the injection, BRIXADI changes to a gel form called a depot. The depot is not always felt under the skin.
- Do not try to remove the depot.
- If you miss a dose of BRIXADI, see your healthcare provider to get your BRIXADI injection as soon as possible.

What should I avoid while receiving BRIXADI?

- Do not drive, operate heavy machinery or perform any other dangerous activities until you know how BRIXADI affects you. BRIXADI can cause drowsiness and slow reaction times. BRIXADI can make you sleepy, dizzy, or lightheaded. This may happen more often in the first few days after your injection and when your dose is being changed.
- You should not drink alcohol or use prescription or over-the-counter medicines that contain alcohol during treatment with BRIXADI, because this can lead to loss of consciousness or even death.

What are the possible side effects of BRIXADI?
BRIXADI can cause serious side effects, including:

- Trouble breathing. Taking BRIXADI with other opioid medicines, benzodiazepines, gabapentinoids (gabapentin or pregabalin), alcohol, or other central nervous system depressants (including street drugs) can cause breathing problems that can lead to coma and death.
- Sleepiness, dizziness, and problems with coordination.
- Physical dependence or abuse.
- Liver problems. Call your healthcare provider right away if you notice any of these symptoms:
  - your skin or the white part of your eyes turns yellow (jaundice)
  - dark or "tea colored" urine
  - light colored stools (bowel movements)
  - loss of appetite
  - ain, aching, or tenderness on the right side of your stomach-area
  - nausea

Your healthcare provider should do tests to check your liver before and during treatment with BRIXADI.

- Allergic reaction. You may have a rash, hives, swelling of your face, wheezing, light-headedness when changing positions, feeling faint, or loss of consciousness. Call your healthcare provider or get emergency help right away.
- Opioid withdrawal. Call your healthcare provider right away if you get any of these symptoms:
  - shaking
  - sweating more than normal
  - feeling hot or cold more than normal
  - runny nose
  - watery eyes
  - goose bumps
  - diarrhea
  - vomiting
  - muscle aches

These symptoms may start weeks to months after your last dose of BRIXADI. Tell your healthcare provider if you develop any of these symptoms.

- Decrease in blood pressure. You may feel dizzy if you get up too fast from sitting or lying down.

The most common side effects of BRIXADI include:

- injection site pain
- headache
- constipation
- nausea
- injection site redness
- injection site itching
- trouble sleeping (insomnia)
- urinary tract infection

BRIXADI may affect fertility in males and females. Talk to your healthcare provider if this is a concern for you.
These are not all of the possible side effects of BRIXADI.
Call your doctor for medical advice about side effects. You may report side effects to FDA at 1-800-FDA-1088.

General information about the safe and effective use of BRIXADI.
Medicines are sometimes prescribed for purposes other than those listed in a Medication Guide. You can ask your pharmacist or healthcare provider for information that is written for healthcare professionals.

What are the ingredients in BRIXADI?
Active ingredient: buprenorphine
Inactive ingredients:
BRIXADI weekly: anhydrous ethanol and soybean phosphatidylcholine/glycerol dioleate.
BRIXADI monthly: N-methyl pyrrolidine and soybean phosphatidylcholine/glycerol dioleate.

Distributed by Braeburn, Inc., Plymouth Meeting, PA 19462, USA.
© 2025 Braeburn, Inc. BRIXADI® is a registered trademark of Braeburn Inc.
Manufactured by: Pharmaceutics International, Inc. (Pii), Cockeysville MD 21030
For more information, go to www.BRIXADI.com or call 1-833-274-9234

This Medication Guide has been approved by the U. S. Food and Drug Administration.
BRX-MG-002

Issued: 12/2025

PACKAGE LABEL

Carton - Single-dose Prefilled Syringe Kit - 8 mg Weekly Dose - BRIXADI

PRINCIPAL DISPLAY PANEL

Brixadi®
(buprenorphine) extended-release
injection for subcutaneous use
CIII
WEEKLY

For Subcutaneous Use Only

8 mg
0.16 mL
of a 50 mg/mL solution
per syringe (Weekly)

WARNING: SERIOUS HARM OR DEATH COULD
RESULT IF INJECTED INTRAVENOUSLY.

SINGLE-DOSE PREFILLED SYRINGE KIT
CONTENTS:

- One (1) sterile prefilled syring with needle shield. 8 mg (buprenorphine) per syringe
- One (1) plunger rod
- Prescribing Information
- Instructions for Use
- Medication Guide

For Healthcare Provider
Administration Only.
Do Not Dispense to Patient.

Attention: Dispense the enclosed
Medication Giude to each patient.
Rx ONLY
Distributed by: Braeburn Inc.
Plymouth Meeting, PA 19462
Properly dispose of BRIXADI® syringes per facility
procedure for a Schedule III drug product, and per
applicable federal, state, and local regulations.
Once-weekly subcutaneous injection for
treatment of opiod use disorder. For questions,
call 1-833-274-9234.

05/23

NDC 58284-208-01

PACKAGE LABEL

Carton - Single-dose Prefilled Syringe Kit - 16 mg Weekly Dose - BRIXADI

PRINCIPAL DISPLAY PANEL

Brixadi®
(buprenorphine) extended-release
injection for subcutaneous use
CIII
WEEKLY

For Subcutaneous Use Only

16 mg
0.32 mL
of a 50 mg/mL solution
per syringe (Weekly)

WARNING: SERIOUS HARM OR DEATH COULD
RESULT IF INJECTED INTRAVENOUSLY.

SINGLE-DOSE PREFILLED SYRINGE KIT
CONTENTS:

- One (1) sterile prefilled syring with needle shield. 16 mg (buprenorphine) per syringe
- One (1) plunger rod
- Prescribing Information
- Instructions for Use
- Medication Guide

For Healthcare Provider
Administration Only.
Do Not Dispense to Patient.

Attention: Dispense the enclosed
Medication Giude to each patient.
Rx ONLY
Distributed by: Braeburn Inc.
Plymouth Meeting, PA 19462
Properly dispose of BRIXADI® syringes per facility
procedure for a Schedule III drug product, and per
applicable federal, state, and local regulations.
Once-weekly subcutaneous injection for
treatment of opiod use disorder. For questions,
call 1-833-274-9234.

05/23

NDC 58284-216-01

PACKAGE LABEL

Carton - Single-dose Prefilled Syringe Kit - 24 mg Weekly Dose - BRIXADI

PRINCIPAL DISPLAY PANEL

Brixadi®
(buprenorphine) extended-release
injection for subcutaneous use
CIII
WEEKLY

For Subcutaneous Use Only

24 mg
0.48 mL
of a 50 mg/mL solution
per syringe (Weekly)

WARNING: SERIOUS HARM OR DEATH COULD
RESULT IF INJECTED INTRAVENOUSLY.

SINGLE-DOSE PREFILLED SYRINGE KIT
CONTENTS:

- One (1) sterile prefilled syring with needle shield. 24 mg (buprenorphine) per syringe
- One (1) plunger rod
- Prescribing Information
- Instructions for Use
- Medication Guide

For Healthcare Provider
Administration Only.
Do Not Dispense to Patient.

Attention: Dispense the enclosed
Medication Giude to each patient.
Rx ONLY
Distributed by: Braeburn Inc.
Plymouth Meeting, PA 19462
Properly dispose of BRIXADI® syringes per facility
procedure for a Schedule III drug product, and per
applicable federal, state, and local regulations.
Once-weekly subcutaneous injection for
treatment of opiod use disorder. For questions,
call 1-833-274-9234.

05/23

NDC 58284-224-01

PACKAGE LABEL

Carton - Single-dose Prefilled Syringe Kit - 32 mg Weekly Dose - BRIXADI

PRINCIPAL DISPLAY PANEL

Brixadi®
(buprenorphine) extended-release
injection for subcutaneous use
CIII
WEEKLY

For Subcutaneous Use Only

32 mg
0.64 mL
of a 50 mg/mL solution
per syringe (Weekly)

WARNING: SERIOUS HARM OR DEATH COULD
RESULT IF INJECTED INTRAVENOUSLY.

SINGLE-DOSE PREFILLED SYRINGE KIT
CONTENTS:

- One (1) sterile prefilled syring with needle shield. 32 mg (buprenorphine) per syringe
- One (1) plunger rod
- Prescribing Information
- Instructions for Use
- Medication Guide

For Healthcare Provider
Administration Only.
Do Not Dispense to Patient.

Attention: Dispense the enclosed
Medication Giude to each patient.
Rx ONLY
Distributed by: Braeburn Inc.
Plymouth Meeting, PA 19462
Properly dispose of BRIXADI® syringes per facility
procedure for a Schedule III drug product, and per
applicable federal, state, and local regulations.
Once-weekly subcutaneous injection for
treatment of opiod use disorder. For questions,
call 1-833-274-9234.

05/23

NDC 58284-232-01

PACKAGE LABEL

Carton - Single-dose Prefilled Syringe Kit - 64 mg Monthly Dose - BRIXADI

PRINCIPAL DISPLAY PANEL

Brixadi®
(buprenorphine) extended-release
injection for subcutaneous use
CIII
MONTHLY

For Subcutaneous Use Only

64 mg
0.18 mL
of a 356 mg/mL solution
per syringe (Monthly)

WARNING: SERIOUS HARM OR DEATH COULD
RESULT IF INJECTED INTRAVENOUSLY.

SINGLE-DOSE PREFILLED SYRINGE KIT
CONTENTS:

- One (1) sterile prefilled syring with needle shield. 64 mg (buprenorphine) per syringe
- One (1) plunger rod
- Prescribing Information
- Instructions for Use
- Medication Guide

For Healthcare Provider
Administration Only.
Do Not Dispense to Patient.

Attention: Dispense the enclosed
Medication Giude to each patient.
Rx ONLY
Distributed by: Braeburn Inc.
Plymouth Meeting, PA 19462
Properly dispose of BRIXADI® syringes per facility
procedure for a Schedule III drug product, and per
applicable federal, state, and local regulations.
Once-monthly subcutaneous injection for
treatment of opiod use disorder. For questions,
call 1-833-274-9234.

05/23

NDC 58284-264-01

PACKAGE LABEL

Carton - Single-dose Prefilled Syringe Kit - 96 mg Monthly Dose - BRIXADI

PRINCIPAL DISPLAY PANEL

Brixadi®
(buprenorphine) extended-release
injection for subcutaneous use
CIII
MONTHLY

For Subcutaneous Use Only

96 mg
0.27 mL
of a 356 mg/mL solution
per syringe (Monthly)

WARNING: SERIOUS HARM OR DEATH COULD
RESULT IF INJECTED INTRAVENOUSLY.

SINGLE-DOSE PREFILLED SYRINGE KIT
CONTENTS:

- One (1) sterile prefilled syring with needle shield. 96 mg (buprenorphine) per syringe
- One (1) plunger rod
- Prescribing Information
- Instructions for Use
- Medication Guide

For Healthcare Provider
Administration Only.
Do Not Dispense to Patient.

Attention: Dispense the enclosed
Medication Giude to each patient.
Rx ONLY
Distributed by: Braeburn Inc.
Plymouth Meeting, PA 19462
Properly dispose of BRIXADI® syringes per facility
procedure for a Schedule III drug product, and per
applicable federal, state, and local regulations.
Once-monthly subcutaneous injection for
treatment of opiod use disorder. For questions,
call 1-833-274-9234.

05/23

NDC 58284-296-01

PACKAGE LABEL

Carton - Single-dose Prefilled Syringe Kit - 128 mg Monthly Dose - BRIXADI

PRINCIPAL DISPLAY PANEL

Brixadi®
(buprenorphine) extended-release
injection for subcutaneous use
CIII
MONTHLY

For Subcutaneous Use Only

128 mg
0.36 mL
of a 356 mg/mL solution
per syringe (Monthly)

WARNING: SERIOUS HARM OR DEATH COULD
RESULT IF INJECTED INTRAVENOUSLY.

SINGLE-DOSE PREFILLED SYRINGE KIT
CONTENTS:

- One (1) sterile prefilled syring with needle shield. 128 mg (buprenorphine) per syringe
- One (1) plunger rod
- Prescribing Information
- Instructions for Use
- Medication Guide

For Healthcare Provider
Administration Only.
Do Not Dispense to Patient.

Attention: Dispense the enclosed
Medication Giude to each patient.
Rx ONLY
Distributed by: Braeburn Inc.
Plymouth Meeting, PA 19462
Properly dispose of BRIXADI® syringes per facility
procedure for a Schedule III drug product, and per
applicable federal, state, and local regulations.
Once-monthly subcutaneous injection for
treatment of opiod use disorder. For questions,
call 1-833-274-9234.

05/23

NDC 58284-228-01